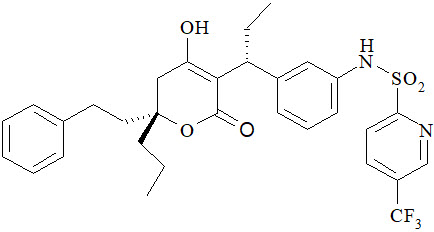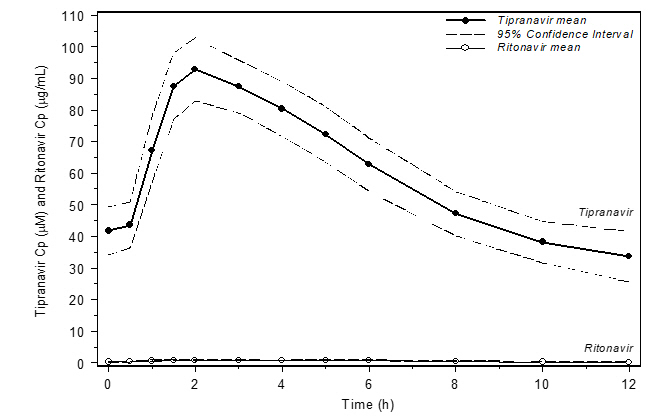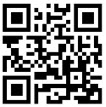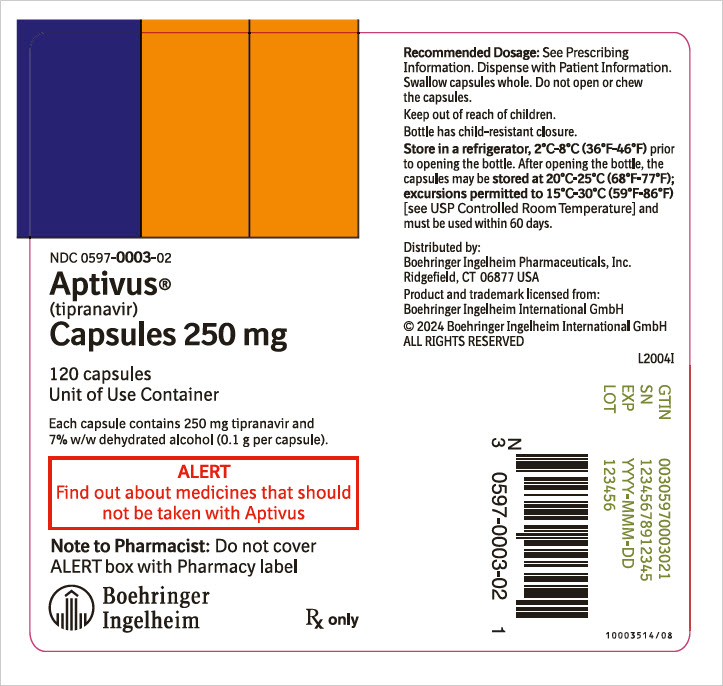 DRUG LABEL: Aptivus
NDC: 0597-0003 | Form: CAPSULE, LIQUID FILLED
Manufacturer: Boehringer Ingelheim Pharmaceuticals, Inc.
Category: prescription | Type: HUMAN PRESCRIPTION DRUG LABEL
Date: 20250618

ACTIVE INGREDIENTS: TIPRANAVIR 250 mg/1 1

HIGHLIGHTS OF PRESCRIBING INFORMATION

These highlights do not include all the information needed to use APTIVUS safely and effectively. See full prescribing information for APTIVUS.
APTIVUS® (tipranavir) capsules, for oral use
Initial U.S. Approval: 2005

WARNING: HEPATOTOXICITY and INTRACRANIAL HEMORRHAGE

See full prescribing information for complete boxed warning.

- Clinical hepatitis and hepatic decompensation including some fatalities. Extra vigilance is warranted in patients with chronic hepatitis B or hepatitis C co-infection. (5.2)
- Fatal and non-fatal intracranial hemorrhage (5.3)

RECENT MAJOR CHANGES

Indications and Usage (1) | 04/2024
Dosage and Administration (2.1, 2.2) | 04/2024
Warnings and Precautions, Co-administration with Ritonavir (5.1) | 04/2024
Warnings and Precautions, Platelet Aggregation and Coagulation (5.5) | 04/2024
Warnings and Precautions, Vitamin E Intake (5.5) Removed | 04/2024

1 INDICATIONS AND USAGE

APTIVUS, a protease inhibitor, co-administered with ritonavir, is indicated for combination antiretroviral treatment of HIV-1 infected adult and pediatric patients weighing 36 kg or higher who are treatment-experienced and infected with HIV-1 strains resistant to more than one protease inhibitor (1)

- Do not use APTIVUS/ritonavir in treatment-naïve patients (1)

2 DOSAGE AND ADMINISTRATION

- Adults: 500 mg APTIVUS, co-administered with 200 mg ritonavir, twice daily (2.2)
- Pediatric patients (weighing 36 kg or higher): 500 mg APTIVUS, co-administered with 200 mg ritonavir twice daily. (2.2)
- APTIVUS taken with ritonavir tablets must be taken with meals (2.1)
- APTIVUS capsules must be swallowed whole and must not be opened or chewed (2.1)
- Children should be assessed for their ability to swallow capsules before prescribing APTIVUS capsules. (2.1)
- Store unopened bottles of APTIVUS capsules in the refrigerator. (16)

3 DOSAGE FORMS AND STRENGTHS

- Capsules: 250 mg (3)

4 CONTRAINDICATIONS

- Patients with moderate or severe (Child-Pugh Class B or C) hepatic impairment (4, 5.2)
- Use with drugs highly dependent on CYP3A for clearance or are potent CYP3A inducers (4, 5.4, 7)

5 WARNINGS AND PRECAUTIONS

- Co-administration with Ritonavir: APTIVUS must be co-administered with ritonavir and food to achieve the desired antiviral effect. Failure to administer APTIVUS with ritonavir and food may result in a loss of efficacy of tipranavir. (5.1)
- Hepatic Impairment: Discontinue for signs and symptoms of clinical hepatitis or asymptomatic increases in ALT/AST >10 times ULN or asymptomatic increases in ALT/AST 5-10 times ULN with concomitant increases in total bilirubin. Monitor liver function tests prior to therapy and frequently thereafter. (5.2)
- Intracranial Hemorrhage/Platelet Aggregation and Coagulation: Use with caution in patients at risk for increased bleeding or who are receiving medications that increase the risk of bleeding. (5.3, 5.5)
- The concomitant use of APTIVUS/ritonavir and certain other drugs may result in known or potentially significant drug interactions. Consult the full prescribing information prior to and during treatment for potential drug interactions. (5.4, 7.2)
- Rash: Discontinue and initiate appropriate treatment if severe skin reaction occurs or is suspected. (5.6) Use with caution in patients with a known sulfonamide allergy. (5.7)
- Patients may develop new onset or exacerbations of diabetes mellitus, hyperglycemia (5.8), immune reconstitution syndrome (5.9), redistribution/accumulation of body fat (5.10), and elevated lipids. (5.11) Monitor cholesterol and triglycerides prior to therapy and periodically thereafter.
- Hemophilia: Spontaneous bleeding may occur, and additional factor VIII may be required. (5.12)

6 ADVERSE REACTIONS

- In adults the most frequent adverse reactions (incidence >4%) were diarrhea, nausea, pyrexia, vomiting, fatigue, headache, and abdominal pain. (6.1)
- In pediatric subjects the most frequent adverse reactions were generally similar to those seen in adults. However, rash was more frequent in pediatric subjects than in adults. (6.2)

To report SUSPECTED ADVERSE REACTIONS, contact Boehringer Ingelheim Pharmaceuticals, Inc. at 1-800-542-6257 or FDA at 1-800-FDA-1088 or www.fda.gov/medwatch.

7 DRUG INTERACTIONS

Co-administration of APTIVUS can alter the concentrations of other drugs and other drugs may alter the concentration of tipranavir. The potential for drug-drug interactions must be considered prior to and during therapy. (4, 5.4, 7)

FULL PRESCRIBING INFORMATION

WARNING: HEPATOTOXICITY and INTRACRANIAL HEMORRHAGE

Hepatotoxicity:

Clinical hepatitis and hepatic decompensation, including some fatalities, have been reported. Extra vigilance is warranted in patients with chronic hepatitis B or hepatitis C co-infection, as these patients have an increased risk of hepatotoxicity [see Warnings and Precautions (5.2)].

Intracranial Hemorrhage:

Both fatal and non-fatal intracranial hemorrhage have been reported [see Warnings and Precautions (5.3)].

1 INDICATIONS AND USAGE

APTIVUS, co-administered with ritonavir, is indicated for combination antiretroviral treatment of HIV-1 infected adults and pediatric patients weighing 36 kg or higher who are treatment-experienced and infected with HIV-1 strains resistant to more than one protease inhibitor (PI) [see Use in Specific Populations (8.4)].

This indication is based on analyses of plasma HIV-1 RNA levels in two controlled studies of APTIVUS/ritonavir of 48 weeks duration in treatment-experienced adults and one open-label 48-week study in pediatric patients. The adult studies were conducted in clinically advanced, 3-class antiretroviral (NRTI, NNRTI, PI) treatment-experienced adults with evidence of HIV-1 replication despite ongoing antiretroviral therapy.

The following points should be considered when initiating therapy with APTIVUS/ritonavir:

- The use of APTIVUS/ritonavir in treatment-naïve patients is not recommended [see Warnings and Precautions (5.2)].
- The use of other active agents with APTIVUS/ritonavir is associated with a greater likelihood of treatment response [see Microbiology (12.4) and Clinical Studies (14)].
- Genotypic or phenotypic testing and/or treatment history should guide the use of APTIVUS/ritonavir [see Microbiology (12.4)]. The number of baseline primary protease inhibitor mutations affects the virologic response to APTIVUS/ritonavir [see Microbiology (12.4)].
- Use caution when prescribing APTIVUS/ritonavir to patients with elevated transaminases, hepatitis B or C co-infection or patients with mild hepatic impairment [see Warnings and Precautions (5.2)].
- Liver function tests should be performed at initiation of therapy with APTIVUS/ritonavir and monitored frequently throughout the duration of treatment [see Warnings and Precautions (5.2)].
- The drug-drug interaction potential of APTIVUS/ritonavir when co-administered with other drugs must be considered prior to and during APTIVUS/ritonavir use [see Contraindications (4) and Drug Interactions (7)].
- Use caution when prescribing APTIVUS/ritonavir in patients who may be at risk for increased bleeding or who are receiving medications known to increase the risk of bleeding [see Warnings and Precautions (5.5)].

There are no study results demonstrating the effect of APTIVUS/ritonavir on clinical progression of HIV-1.

2 DOSAGE AND ADMINISTRATION

2.1 Dosage and Administration Overview

APTIVUS must be co-administered with ritonavir to exert its therapeutic effect. Failure to correctly co-administer APTIVUS with ritonavir will result in plasma levels of tipranavir that will be insufficient to achieve the desired antiviral effect and will alter some drug interactions [see Warnings and Precautions (5.1)].

- Children should be assessed for their ability to swallow capsules before prescribing APTIVUS capsules [see Use in Specific Populations (8.4)].
- APTIVUS co-administered with ritonavir tablets must only be taken with meals [see Clinical Pharmacology (12.3)].
- APTIVUS is supplied as capsules. APTIVUS capsules must be swallowed whole and must not be opened or chewed.
- Due to the need for co-administration of APTIVUS with ritonavir, please refer to the ritonavir prescribing information.

2.2 Recommended Dosage in Adults and Pediatric Patients Weighing 36 kg or Higher

The recommended dosage in adults and pediatric patients weighing 36 kg or higher is 500 mg (two 250 mg capsules) of APTIVUS co-administered with 200 mg of ritonavir, twice daily.

3 DOSAGE FORMS AND STRENGTHS

Capsules: 250 mg, pink, oblong capsules imprinted with "TPV 250"

4 CONTRAINDICATIONS

- APTIVUS is contraindicated in patients with moderate or severe (Child-Pugh Class B or C, respectively) hepatic impairment [see Warnings and Precautions (5.2)].
- APTIVUS/ritonavir is contraindicated when co-administered with drugs that are highly dependent on CYP3A for clearance or are potent CYP3A inducers (see Table 1) [see Drug Interactions (7.2)].

Table 1 Drugs that are Contraindicated with APTIVUS Co-Administered with Ritonavir
Drug Class | Drugs within Class that are Contraindicated with APTIVUS Co-administered with Ritonavir | Clinical Comments:
Alpha 1-adrenoreceptor antagonist | Alfuzosin | Potentially increased alfuzosin concentrations can result in hypotension.
Antiarrhythmics | Amiodarone, bepridil, flecainide, propafenone, quinidine | Potential for serious and/or life-threatening reactions such as cardiac arrhythmias secondary to increases in plasma concentrations of antiarrhythmics.
Antimycobacterials | Rifampin | May lead to loss of virologic response and possible resistance to APTIVUS or to the class of protease inhibitors or other co-administered antiretroviral agents.
Ergot derivatives | Dihydroergotamine, ergonovine, ergotamine, methylergonovine | Potential for acute ergot toxicity characterized by peripheral vasospasm and ischemia of the extremities and other tissues.
GI motility agent | Cisapride | Potential for cardiac arrhythmias.
Herbal products | St. John's wort (hypericum perforatum) | May lead to loss of virologic response and possible resistance to APTIVUS or to the class of protease inhibitors.
HMG CoA reductase inhibitors | Lovastatin, simvastatin | Potential for myopathy including rhabdomyolysis.
Antipsychotics | Pimozide | Potential for cardiac arrhythmias.
 | Lurasidone | Potential for serious and/or life-threatening reactions.
PDE-5 inhibitors | Sildenafil (Revatio) [for treatment of pulmonary arterial hypertension] | A safe and effective dose has not been established when used with APTIVUS/ritonavir. There is increased potential for sildenafil-associated adverse events (which include visual disturbances, hypotension, prolonged erection, and syncope).
Sedatives/hypnotics | Oral midazolam, triazolam | Prolonged or increased sedation or respiratory depression.

Due to the need for co-administration of APTIVUS with ritonavir, please refer to the ritonavir prescribing information for a description of ritonavir contraindications.

5 WARNINGS AND PRECAUTIONS

5.1 Importance of Co-administration with Ritonavir

APTIVUS must be co-administered with ritonavir and food to achieve the desired antiviral effect. Failure to administer APTIVUS with ritonavir and food may result in a loss of efficacy of tipranavir. Please refer to the ritonavir prescribing information for additional information on precautionary measures.

5.2 Hepatic Impairment and Toxicity

Clinical hepatitis and hepatic decompensation, including some fatalities, were reported with APTIVUS co-administered with 200 mg of ritonavir. These have generally occurred in subjects with advanced HIV-1 disease taking multiple concomitant medications. A causal relationship to APTIVUS/ritonavir could not be established. Physicians and patients should be vigilant for the appearance of signs or symptoms of hepatitis, such as fatigue, malaise, anorexia, nausea, jaundice, bilirubinuria, acholic stools, liver tenderness or hepatomegaly. Patients with signs or symptoms of clinical hepatitis should discontinue APTIVUS/ritonavir treatment and seek medical evaluation.

All patients should be followed closely with clinical and laboratory monitoring, especially those with chronic hepatitis B or C co-infection, as these patients have an increased risk of hepatotoxicity. Liver function tests should be performed prior to initiating therapy with APTIVUS/ritonavir, and frequently throughout the duration of treatment.

If asymptomatic elevations in AST or ALT greater than 10 times the upper limit of normal occur, APTIVUS/ritonavir therapy should be discontinued. If asymptomatic elevations in AST or ALT between 5 – 10 times the upper limit of normal and increases in total bilirubin greater than 2.5 times the upper limit of normal occur, APTIVUS/ritonavir therapy should be discontinued.

Treatment-experienced patients with chronic hepatitis B or hepatitis C co-infection or elevated transaminases are at approximately 2-fold risk for developing Grade 3 or 4 transaminase elevations or hepatic decompensation. In two large, randomized, open-label, controlled clinical trials with an active comparator (1182.12 and 1182.48) of treatment-experienced subjects, Grade 3 and 4 increases in hepatic transaminases were observed in 10.3% (10.9/100 PEY) receiving APTIVUS/ritonavir through week 48. In a study of treatment-naïve subjects, 20.3% (21/100 PEY) experienced Grade 3 or 4 hepatic transaminase elevations while receiving APTIVUS/ritonavir 500 mg/200 mg through week 48.

Tipranavir is principally metabolized by the liver. Caution should be exercised when administering APTIVUS/ritonavir to patients with mild hepatic impairment (Child-Pugh Class A) because tipranavir concentrations may be increased [see Clinical Pharmacology (12.3)].

5.3 Intracranial Hemorrhage

APTIVUS, co-administered with 200 mg of ritonavir, has been associated with reports of both fatal and non-fatal intracranial hemorrhage (ICH). Many of these subjects had other medical conditions or were receiving concomitant medications that may have caused or contributed to these events. No pattern of abnormal coagulation parameters has been observed in subjects in general, or preceding the development of ICH. Therefore, routine measurement of coagulation parameters is not currently indicated in the management of patients on APTIVUS.

5.4 Risk of Serious Adverse Reactions Due to Drug Interactions

Initiation of APTIVUS/ritonavir, a CYP3A inhibitor, in patients receiving medications metabolized by CYP3A or initiation of medications metabolized by CYP3A in patients already receiving APTIVUS/ritonavir, may increase plasma concentrations of medications metabolized by CYP3A. Initiation of medications that inhibit or induce CYP3A may increase or decrease concentrations of APTIVUS/ritonavir, respectively. These interactions may lead to:

- Clinically significant adverse reactions, potentially leading to severe, life-threatening, or fatal events from greater exposures of concomitant medications.
- Clinically significant adverse reactions from greater exposures of APTIVUS/ritonavir.
- Loss of therapeutic effect of APTIVUS/ritonavir and possible development of resistance.

See Table 4 for steps to prevent or manage these possible and known significant drug interactions, including dosing recommendations [see Drug Interactions (7)]. Consider the potential for drug interactions prior to and during APTIVUS/ritonavir therapy; review concomitant medications during APTIVUS/ritonavir therapy; and monitor for the adverse reactions associated with the concomitant medications [see Contraindications (4) and Drug Interactions (7)].

5.5 Effects on Platelet Aggregation and Coagulation

APTIVUS/ritonavir should be used with caution in patients who may be at risk of increased bleeding from trauma, surgery or other medical conditions, or who are receiving medications known to increase the risk of bleeding such as antiplatelet agents and anticoagulants, or who are taking supplemental high doses of vitamin E.

In rats, tipranavir treatment alone induced dose-dependent changes in coagulation parameters, bleeding events and death. Co-administration with vitamin E significantly increased these effects [see Nonclinical Toxicology (13.2)]. However, analyses of stored plasma from adult and pediatric subjects treated with APTIVUS capsules plus low-dose ritonavir showed no effect of APTIVUS/ritonavir on vitamin K-dependent coagulation factors (Factor II and Factor VII), Factor V, or on prothrombin or activated partial thromboplastin times.

In in vitro experiments, tipranavir was observed to inhibit human platelet aggregation at levels consistent with exposures observed in subjects receiving APTIVUS/ritonavir.

5.6 Rash

Rash, including urticarial rash, maculopapular rash, and possible photosensitivity, has been reported in subjects receiving APTIVUS/ritonavir. In some cases rash was accompanied by joint pain or stiffness, throat tightness, or generalized pruritus. In controlled adult clinical trials, rash (all grades, all causality) was observed in 10% of females and in 8% of males receiving APTIVUS/ritonavir through 48 weeks of treatment. The median time to onset of rash was 53 days and the median duration of rash was 22 days. The discontinuation rate for rash in clinical trials was 0.5%. In an uncontrolled compassionate use program (n=3920), cases of rash, some of which were severe, accompanied by myalgia, fever, erythema, desquamation, and mucosal erosions were reported. In the pediatric clinical trial, the frequency of rash (all grades, all causality) through 48 weeks of treatment was 21%. Overall, most of the pediatric subjects had mild rash and 5 (5%) had moderate rash. Overall 3% of pediatric subjects interrupted APTIVUS treatment due to rash and the discontinuation rate for rash in pediatric subjects was 0.9%. Discontinue and initiate appropriate treatment if severe skin rash develops.

5.7 Sulfa Allergy

APTIVUS should be used with caution in patients with a known sulfonamide allergy. Tipranavir contains a sulfonamide moiety. The potential for cross-sensitivity between drugs in the sulfonamide class and APTIVUS is unknown.

5.8 Diabetes Mellitus/Hyperglycemia

New onset diabetes mellitus, exacerbation of pre-existing diabetes mellitus and hyperglycemia have been reported during post-marketing surveillance in HIV-1 infected patients receiving protease inhibitor therapy. Some patients required either initiation or dose adjustments of insulin or oral hypoglycemic agents for treatment of these events. In some cases, diabetic ketoacidosis has occurred. In those patients who discontinued protease inhibitor therapy, hyperglycemia persisted in some cases. Because these events have been reported voluntarily during clinical practice, estimates of frequency cannot be made and a causal relationship between protease inhibitor therapy and these events has not been established.

5.9 Immune Reconstitution Syndrome

Immune reconstitution syndrome has been reported in patients treated with combination antiretroviral therapy, including APTIVUS. During the initial phase of combination antiretroviral treatment, patients whose immune system responds may develop an inflammatory response to indolent or residual opportunistic infections (such as Mycobacterium avium infection, cytomegalovirus, Pneumocystis jiroveci pneumonia, tuberculosis, or reactivation of herpes simplex and herpes zoster), which may necessitate further evaluation and treatment.

Autoimmune disorders (such as Graves' disease, polymyositis, and Guillain-Barré syndrome) have also been reported to occur in the setting of immune reconstitution, however, the time to onset is more variable, and can occur many months after initiation of treatment.

5.10 Fat Redistribution

Redistribution/accumulation of body fat including central obesity, dorsocervical fat enlargement (buffalo hump), peripheral wasting, facial wasting, breast enlargement, and "cushingoid appearance" have been observed in patients receiving antiretroviral therapy. The mechanism and long-term consequences of these events are currently unknown. A causal relationship has not been established.

5.11 Elevated Lipids

Treatment with APTIVUS co-administered with 200 mg of ritonavir has resulted in large increases in the concentration of total cholesterol and triglycerides [see Adverse Reactions (6)]. Triglyceride and cholesterol testing should be performed prior to initiating APTIVUS/ritonavir therapy and at periodic intervals during therapy. Lipid disorders should be managed as clinically appropriate; taking into account any potential drug-drug interactions [see Drug Interactions (7.2)].

5.12 Patients with Hemophilia

There have been reports of increased bleeding, including spontaneous skin hematomas and hemarthrosis in patients with hemophilia type A and B treated with protease inhibitors. In some patients additional Factor VIII was given. In more than half of the reported cases, treatment with protease inhibitors was continued or reintroduced if treatment had been discontinued. A causal relationship between protease inhibitors and these events has not been established.

5.13 Resistance/Cross Resistance

Because the potential for HIV-1 cross-resistance among protease inhibitors has not been fully explored in APTIVUS/ritonavir treated patients, it is unknown what effect therapy with APTIVUS will have on the activity of subsequently administered protease inhibitors.

6 ADVERSE REACTIONS

The following adverse reactions are described, in greater detail, in other sections:

- Hepatic Impairment and Toxicity [see Warnings and Precautions (5.2)]
- Intracranial Hemorrhage [see Warnings and Precautions (5.3)]
- Rash [see Warnings and Precautions (5.6)]

Due to the need for co-administration of APTIVUS with ritonavir, please refer to ritonavir prescribing information for ritonavir-associated adverse reactions.

Because clinical trials are conducted under widely varying conditions, adverse reaction rates observed in the clinical trials of a drug cannot be directly compared to rates in the clinical trials of another drug and may not reflect the rates observed in clinical practice.

6.1 Clinical Trials in Adults

APTIVUS, co-administered with ritonavir, has been studied in a total of 6308 HIV-1 positive adults as combination therapy in clinical studies. Of these, 1299 treatment-experienced subjects received the dose of 500 mg/200 mg BID. Nine hundred nine (909) adults, including 541 in the 1182.12 and 1182.48 controlled clinical trials, have been treated for at least 48 weeks [see Clinical Studies (14)].

In 1182.12 and 1182.48 in the APTIVUS/ritonavir arm, the most frequent adverse reactions were diarrhea, nausea, pyrexia, vomiting, fatigue, headache, and abdominal pain. The 48-Week Kaplan-Meier rates of adverse reactions leading to discontinuation were 13.3% for APTIVUS/ritonavir-treated subjects and 10.8% for the comparator arm subjects.

Adverse reactions reported in the controlled clinical trials 1182.12 and 1182.48, based on treatment-emergent clinical adverse reactions of moderate to severe intensity (Grades 2 - 4) in at least 2% of treatment-experienced subjects in either treatment group are summarized in Table 2 below.

Table 2 Adverse Reactions Reported in Randomized, Controlled Clinical Trials (1182.12 and 1182.48) Based on Treatment-Emergent Clinical Adverse Reactions of Moderate to Severe Intensity (Grades 2 - 4) in at least 2% of Treatment-Experienced Subjects in either Treatment Groupa (48-week Analyses)
 | Percentage of patients (rate per 100 patient-exposure years)
 | APTIVUS/ritonavir (500/200 mg BID) + OBRc (n=749; 757.4 patient-exposure years) | Comparator PI/ritonavirb + OBR (n=737; 503.9 patient-exposure years)
Blood and Lymphatic Disorders
Anemia | 3.3% (3.4) | 2.3% (3.4)
Neutropenia | 2.0% (2.0) | 1.0% (1.4)
Gastrointestinal Disorders
Diarrhea | 15.0% (16.5) | 13.4% (21.6)
Nausea | 8.5% (9.0) | 6.4% (9.7)
Vomiting | 5.9% (6.0) | 4.1% (6.1)
Abdominal pain | 4.4% (4.5) | 3.4% (5.1)
Abdominal pain upper | 1.5% (1.5) | 2.3% (3.4)
General Disorders
Pyrexia | 7.5% (7.7) | 5.4% (8.2)
Fatigue | 5.7% (5.9) | 5.6% (8.4)
Investigations
Weight decreased | 3.1% (3.1) | 2.2% (3.2)
ALT increased | 2.0% (2.0) | 0.5% (0.8)
GGT increased | 2.0% (2.0) | 0.4% (0.6)
Metabolism and Nutrition Disorders
Hypertriglyceridemia | 3.9% (4.0) | 2.0% (3.0)
Hyperlipidemia | 2.5% (2.6) | 0.8% (1.2)
Dehydration | 2.1% (2.1) | 1.1% (1.6)
Musculoskeletal and Connective Tissue Disorders
Myalgia | 2.3% (2.3) | 1.8% (2.6)
Nervous System Disorders
Headache | 5.2% (5.3) | 4.2% (6.3)
Peripheral neuropathy | 1.5% (1.5) | 2.0% (3.0)
Psychiatric Disorders
Insomnia | 1.7% (1.7) | 3.7% (5.5)
Respiratory, Thoracic and Mediastinal Disorders
Dyspnea | 2.1% (2.1) | 1.0% (1.4)
Skin and Subcutaneous Tissue Disorders
Rash | 3.1% (3.1) | 3.8% (5.7)
aExcludes laboratory abnormalities that were Adverse Events
bComparator PI/ritonavir: lopinavir/ritonavir 400/100 mg BID, indinavir/ritonavir 800/100 mg BID, saquinavir/ritonavir 1000/100 mg BID, amprenavir/ritonavir 600/100 mg BID
cOptimized Background Regimen

Less Common Adverse Reactions

Other adverse reactions reported in <2% of adult subjects (n=1474) treated with APTIVUS/ritonavir 500 mg/200 mg in Phase 2 and 3 clinical trials are listed below by body system:

Blood and Lymphatic System Disorders: thrombocytopenia

Gastrointestinal Disorders: abdominal distension, dyspepsia, flatulence, gastroesophageal reflux disease, pancreatitis

General Disorders: influenza-like illness, malaise

Hepatobiliary Disorders: hepatitis, hepatic failure, hyperbilirubinemia, cytolytic hepatitis, toxic hepatitis, hepatic steatosis

Immune System Disorders: hypersensitivity

Investigations: hepatic enzymes increased, liver function test abnormal, lipase increased

Metabolism and Nutrition Disorders: anorexia, decreased appetite, diabetes mellitus, facial wasting, hyperamylasemia, hypercholesterolemia, hyperglycemia, mitochondrial toxicity

Musculoskeletal and Connective Tissue Disorders: muscle cramp

Nervous System Disorders: dizziness, intracranial hemorrhage, somnolence

Psychiatric Disorders: sleep disorder

Renal and Urinary Disorders: renal insufficiency

Skin and Subcutaneous System Disorders: exanthem, lipoatrophy, lipodystrophy acquired, lipohypertrophy, pruritus

Laboratory Abnormalities

Treatment-emergent laboratory abnormalities reported at 48 weeks in the controlled clinical trials 1182.12 and 1182.48 in adults are summarized in Table 3 below.

Table 3 Treatment-Emergent Laboratory Abnormalities Reported in ≥2% of Adult Patients (48-week Analyses)
 |  | Randomized, Controlled Clinical Trials 1182.12 and 1182.48
 |  | Percentage of Patients (rate per 100 patient-exposure years)
 | Limit | APTIVUS/ritonavir (500/200 mg BID) + OBR (n=738) | Comparator PI/ritonavir + OBR* (n=724)
Hematology
WBC count decrease
Grade 3 | <2.0 × 10^3/µL | 5.4% (5.6) | 4.8% (7.7)
Grade 4 | <1.0 × 10^3/µL | 0.3% (0.3) | 1.1% (1.7)
Chemistry
Amylase
Grade 3 | >2.5 × ULN | 5.7% (5.9) | 6.4% (10.4)
Grade 4 | >5 × ULN | 0.3% (0.3) | 0.7% (1.1)
ALT
Grade 2 | >2.5-5 × ULN | 14.9% (16.5) | 7.5% (12.4)
Grade 3 | >5-10 × ULN | 5.6% (5.7) | 1.7% (2.6)
Grade 4 | >10 × ULN | 4.1% (4.1) | 0.4% (0.7)
AST
Grade 2 | >2.5-5 × ULN | 9.9% (10.5) | 8.0% (13.3)
Grade 3 | >5-10 × ULN | 4.5% (4.6) | 1.4% (2.2)
Grade 4 | >10 × ULN | 1.6% (1.6) | 0.4% (0.6)
ALT and/or AST
Grade 2-4 | >2.5 × ULN | 26.0% (31.5) | 13.7% (23.8)
Cholesterol
Grade 2 | >300 – 400 mg/dL | 15.6% (17.7) | 6.4% (10.5)
Grade 3 | >400 – 500 mg/dL | 3.3% (3.3) | 0.3% (0.4)
Grade 4 | >500 mg/dL | 0.9% (1.0) | 0.1% (0.2)
Triglycerides
Grade 2 | 400 – 750 mg/dL | 35.9% (49.9) | 26.8% (51.0)
Grade 3 | >750 – 1200 mg/dL | 16.9% (19.4) | 8.7% (14.6)
Grade 4 | >1200 mg/dL | 8.0% (8.4) | 4.3% (7.0)
*Comparator PI/ritonavir: lopinavir/ritonavir 400/100 mg BID, indinavir/ritonavir 800/100 mg BID, saquinavir/ritonavir 1000/100 mg BID, amprenavir/ritonavir 600/100 mg BID

In controlled clinical trials 1182.12 and 1182.48 extending up to 96 weeks, the proportion of subjects who developed Grade 2-4 ALT and/or AST elevations increased from 26% at week 48 to 32.1% at week 96 with APTIVUS/ritonavir. The risk of developing transaminase elevations is greater during the first year of therapy.

6.2 Clinical Trials in Pediatrics

APTIVUS, co-administered with ritonavir, has been studied in a total of 135 HIV-1 infected pediatric subjects as combination therapy. Study 1182.14 enrolled HIV-1 infected, treatment-experienced pediatric subjects (with the exception of 3 treatment-naïve subjects), with baseline HIV-1 RNA of at least 1500 copies/mL. One hundred and ten (110) subjects were enrolled in a randomized, open-label 48-week clinical trial (Study 1182.14) and 25 subjects were enrolled in other clinical studies including Expanded Access and Emergency Use Programs.

The adverse reactions profile seen in Study 1182.14 was similar to adults. However, rash (5.5%), was reported more frequently in pediatric subjects than in adults.

The most common Grade 3-4 laboratory abnormalities were increases in CPK (11%), ALT (6.5%), and amylase (7.5%).

7 DRUG INTERACTIONS

7.1 Potential for APTIVUS/ritonavir to Affect Other Drugs

APTIVUS co-administered with ritonavir at the recommended dose is a net inhibitor of CYP3A and may increase plasma concentrations of agents that are primarily metabolized by CYP3A. Thus, co-administration of APTIVUS/ritonavir with drugs highly dependent on CYP3A for clearance and for which elevated plasma concentrations are associated with serious and/or life-threatening events is contraindicated [see Contraindications (4)]. Co-administration with other CYP3A substrates may require a dose adjustment or additional monitoring [see Drug Interactions (7)].

Clinically significant drug-drug interactions of APTIVUS co-administered with ritonavir are summarized in Table 4 below.

A phenotypic cocktail study was conducted with 16 healthy volunteers to quantify the influence of 10 days of APTIVUS/ritonavir capsule administration on the activity of hepatic CYP1A2 (caffeine), 2C9 (warfarin), 2C19 (omeprazole), 2D6 (dextromethorphan) and the activity of intestinal and hepatic CYP3A4/5 (midazolam) and P-glycoprotein (P-gp) (digoxin). This study determined the first-dose and steady-state effects of 500 mg of APTIVUS co-administered with 200 mg of ritonavir twice daily in capsule form.

There was no net effect on CYP2C9 or hepatic P-gp at first dose or steady state. There was no net effect after first dose on CYP1A2, but there was moderate induction at steady state. There was modest inhibition of CYP2C19 at the first dose, but there was marked induction at steady state. Potent inhibition of CYP2D6 and both hepatic and intestinal CYP3A4/5 activities were observed after first dose and steady state.

Intestinal and hepatic P-gp activity was assessed by administering oral and intravenous digoxin, respectively. The digoxin results indicate P-gp was inhibited after the first dose of APTIVUS/ritonavir followed by induction of P-gp over time. Thus, it is difficult to predict the net effect of APTIVUS administered with ritonavir on oral bioavailability and plasma concentrations of drugs that are dual substrates of CYP3A and P-gp. The net effect will vary depending on the relative affinity of the co-administered drugs for CYP3A and P-gp, and the extent of intestinal first-pass metabolism/efflux. An in vitro induction study in human hepatocytes showed an increase in UGT1A1 by tipranavir similar to that evoked by rifampin. The clinical consequences of this finding have not been established.

7.2 Potential for Other Drugs to Affect Tipranavir

Tipranavir is a CYP3A substrate and a P-gp substrate. Co-administration of APTIVUS/ritonavir and drugs that induce CYP3A and/or P-gp may decrease tipranavir plasma concentrations. Co-administration of APTIVUS/ritonavir and drugs that inhibit P-gp may increase tipranavir plasma concentrations. Co-administration of APTIVUS/ritonavir with drugs that inhibit CYP3A may not further increase tipranavir plasma concentrations, because the level of metabolites is low following steady-state administration of APTIVUS/ritonavir 500 mg/200 mg twice daily.

Clinically significant drug-drug interactions of APTIVUS co-administered with ritonavir are summarized in Table 4 below [see Contraindications (4), Warnings and Precautions (5.4), and Clinical Pharmacology (12.3)].

Table 4 Established and Other Potentially Significant Drug Interactions: Alterations in Dose or Regimen May be Recommended Based on Drug Interaction Studies or Predicted Interaction
Concomitant Drug Class: Drug name | Effect on Concentration of Tipranavir or Concomitant Drug | Clinical Comment
HIV-1 Antiviral Agents
Fusion Inhibitors:
Enfuvirtide | ↑ Tipranavir | At steady state, tipranavir trough concentrations were approximately 45% higher in patients co-administered enfuvirtide in the Phase 3 trials. The mechanism for this increase is not known. Dose adjustments are not recommended.
Non-Nucleoside Reverse Transcriptase Inhibitors:
Etravirine | ↓ Etravirine | APTIVUS/ritonavir when coadministered with etravirine may cause a significant decrease in the plasma concentrations of etravirine and loss of therapeutic effect of etravirine. Etravirine and APTIVUS/ritonavir should not be coadministered.
Rilpivirine | The use of rilpivirine co-administered with APTIVUS/ritonavir has not been studied. | Concomitant use of rilpivirine with Aptivus/ritonavir may cause an increase in the plasma concentrations of rilpivirine (inhibition of CYP3A enzymes). Rilpivirine is not expected to affect the plasma concentrations of Aptivus/ritonavir.
Nucleoside Reverse Transcriptase Inhibitors:
Abacavir | ↓ Abacavir AUC by approximately 40% | Clinical relevance of reduction in abacavir levels not established. Dose adjustment of abacavir cannot be recommended at this time.
Didanosine (EC) | ↓ Didanosine | Clinical relevance of reduction in didanosine levels not established. For optimal absorption, didanosine should be separated from APTIVUS/ritonavir dosing by at least 2 hours.
Zidovudine | ↓ Zidovudine AUC by approximately 35%. ZDV glucuronide concentrations were unaltered. | Clinical relevance of reduction in zidovudine levels not established. Dose adjustment of zidovudine cannot be recommended at this time.
Protease Inhibitors (co-administered with 200 mg of ritonavir):
Fosamprenavir | ↓ Amprenavir | Combining a protease inhibitor with APTIVUS/ritonavir is not recommended.
Lopinavir | ↓ Lopinavir | Combining a protease inhibitor with APTIVUS/ritonavir is not recommended.
Saquinavir | ↓ Saquinavir | Combining a protease inhibitor with APTIVUS/ritonavir is not recommended.
Protease Inhibitors (co-administered with 100 mg of ritonavir):
Atazanavir | ↓ Atazanavir
 | ↑ Tipranavir
Virus Integrase Strand Transfer Inhibitors (INSTI):
Raltegravir | ↓ Raltegravir | No dose adjustment is needed for 400 mg twice daily dosing regimen of raltegravir. For all other dosing regimens of raltegravir, refer to current prescribing information for raltegravir.
Dolutegravir | ↓ Dolutegravir | For dosage recommendations, refer to dolutegravir prescribing information.
Agents for Opportunistic Infections
Antifungals:
Fluconazole Itraconazole Ketoconazole | ↑ Tipranavir, ↔ Fluconazole | Fluconazole increases tipranavir concentrations but dose adjustments are not needed. Fluconazole doses >200 mg/day are not recommended.
Voriconazole | ↑ Itraconazole (not studied)
 | ↑ Ketoconazole (not studied) | Based on theoretical considerations itraconazole and ketoconazole should be used with caution. High doses (>200 mg/day) are not recommended.
 | ↕ Voriconazole (not studied)
 |  | Due to multiple enzymes involved with voriconazole metabolism, it is difficult to predict the interaction.
Antimycobacterials:
Clarithromycin | ↑ Tipranavir, ↑ Clarithromycin, ↓ 14-hydroxy-clarithromycin metabolite | No dose adjustment of APTIVUS or clarithromycin for patients with normal renal function is necessary.
 |  | For patients with renal impairment the following dosage adjustments should be considered:; - For patients with CLCR 30 to 60 mL/min the dose of clarithromycin should be reduced by 50%. - For patients with CLCR <30 mL/min the dose of clarithromycin should be decreased by 75%.
Rifabutin | Tipranavir not changed, ↑Rifabutin ↑ Desacetyl-rifabutin | Single dose study. Dosage reductions of rifabutin by 75% are recommended (e.g., 150 mg every other day). Increased monitoring for adverse events in patients receiving the combination is warranted. Further dosage reduction may be necessary.
Other Agents Commonly Used
Anticonvulsants:
Carbamazepine Phenobarbital Phenytoin | ↓ Tipranavir | Caution should be used when prescribing carbamazepine, phenobarbital and/or phenytoin. APTIVUS may be less effective due to decreased tipranavir plasma concentration in patients taking these agents concomitantly.
Valproic Acid | ↓ Valproic Acid | Caution should be used when prescribing valproic acid. Valproic acid may be less effective due to decreased valproic acid plasma concentration in patients taking APTIVUS concomitantly.
Antidepressants:
Trazodone | ↑ Trazodone | Concomitant use of trazodone and APTIVUS/ritonavir may increase plasma concentrations of trazodone. Adverse events of nausea, dizziness, hypotension, and syncope have been observed following co-administration of trazodone and ritonavir. If trazodone is used with a CYP3A4 inhibitor such as APTIVUS/ritonavir, the combination should be used with caution and a lower dose of trazodone should be considered.
Desipramine | Combination with APTIVUS/ritonavir not studied ↑ Desipramine | Dosage reduction and concentration monitoring of desipramine is recommended.
Selective Serotonin-Reuptake Inhibitors: | Combination with APTIVUS/ritonavir not studied | Antidepressants have a wide therapeutic index, but doses may need to be adjusted upon initiation of APTIVUS/ritonavir therapy.
Fluoxetine Paroxetine Sertraline | ↑ Fluoxetine ↑ Paroxetine ↑ Sertraline
Anti-gout
Colchicine | ↑ Colchicine | In patients with renal or hepatic impairment, co-administration of colchicine in patients on APTIVUS/ritonavir is contraindicated.
 |  | In combination with APTIVUS/ritonavir, the following dosage adjustments are recommended in patients with normal renal and hepatic function:
 |  | Treatment of gout flares: Co-administration of colchicine in patients on APTIVUS/ritonavir:; - 0.6 mg (1 tablet) × 1 dose, followed by 0.3 mg (half tablet) 1 hour later. Dose to be repeated no earlier than 3 days.
 |  | Prophylaxis of gout flares: Co-administration of colchicine in patients on APTIVUS/ritonavir:; - If the original colchicine regimen was 0.6 mg twice a day, the regimen should be adjusted to 0.3 mg once a day. - If the original colchicine regimen was 0.6 mg once a day, the regimen should be adjusted to 0.3 mg once every other day.
 |  | Treatment of familial Mediterranean fever (FMF): Co-administration of colchicine in patients on APTIVUS/ritonavir:; - Maximum daily dose of 0.6 mg (may be given as 0.3 mg twice a day).
Antipsychotics:
Quetiapine | ↑ Quetiapine | Initiation of APTIVUS with ritonavir in patients taking quetiapine:
 |  | Consider alternative antiretroviral therapy to avoid increases in quetiapine exposures. If co-administration is necessary, reduce the quetiapine dose to 1/6 of the current dose and monitor for quetiapine-associated adverse reactions. Refer to the quetiapine prescribing information for recommendations on adverse reaction monitoring.
 |  | Initiation of quetiapine in patients taking APTIVUS with ritonavir:
 |  | Refer to the quetiapine prescribing information for initial dosing and titration of quetiapine.
Benzodiazepines:
Parenterally administered midazolam | ↑ Midazolam | Midazolam is extensively metabolized by CYP3A4. Increases in the concentration of midazolam are expected to be significantly higher with oral than parenteral administration. Therefore, APTIVUS should not be given with orally administered midazolam [see Contraindications (4)]. If APTIVUS is co-administered with parenteral midazolam, close clinical monitoring for respiratory depression and/or prolonged sedation should be exercised and dosage adjustments should be considered.
Buprenorphine/naloxone | ↔ Buprenorphine ↓ Tipranavir | APTIVUS/ritonavir did not result in changes in the clinical efficacy of buprenorphine/naloxone. Compared to historical controls tipranavir Cmin was decreased approximately 40% with this combination. Dose adjustments cannot be recommended.
Calcium Channel Blockers: | Combination with APTIVUS/ritonavir not studied. Cannot predict effect of TPV/ritonavir on calcium channel blockers that are dual substrates of CYP3A and P-gp due to conflicting effect of TPV/ritonavir on CYP3A and P-gp. | Caution is warranted and clinical monitoring of patients is recommended.
Diltiazem Felodipine Nicardipine Nisoldipine Verapamil | Combination with APTIVUS/ritonavir not studied. Cannot predict effect of TPV/ritonavir on calcium channel blockers that are dual substrates of CYP3A and P-gp due to conflicting effect of TPV/ritonavir on CYP3A and P-gp. | Caution is warranted and clinical monitoring of patients is recommended.
 | ↕ Diltiazem ↑ Felodipine (CYP3A substrate but not P-gp substrate) ↕ Nicardipine ↕ Nisoldipine (CYP3A substrate but not clear whether it is a P-gp substrate) ↕ Verapamil | Caution is warranted and clinical monitoring of patients is recommended.
Disulfiram/Metronidazole | Combination with TPV/ritonavir not studied | APTIVUS capsules contain alcohol that can produce disulfiram-like reactions when co-administered with disulfiram or other drugs which produce this reaction (e.g., metronidazole).
Endothelin receptor antagonists |  | Co-administration of bosentan in patients on APTIVUS/ritonavir:
Bosentan | ↑ Bosentan | In patients who have been receiving APTIVUS/ritonavir for at least 10 days, start bosentan at 62.5 mg once daily or every other day based upon individual tolerability.
 |  | Co-administration of APTIVUS/ritonavir in patients on bosentan:
 |  | Discontinue use of bosentan at least 36 hours prior to initiation of APTIVUS/ritonavir.
 |  | After at least 10 days following the initiation of APTIVUS/ritonavir, resume bosentan at 62.5 mg once daily or every other day based upon individual tolerability.
HMG-CoA Reductase Inhibitors:
Atorvastatin Rosuvastatin | ↑ Atorvastatin ↓ Hydroxy-atorvastatin metabolites ↑ Rosuvastatin | Avoid co-administration with atorvastatin.
Hypoglycemics:
 | Combination with APTIVUS/ritonavir not studied | Careful glucose monitoring is warranted.
Glimepiride Glipizide Glyburide Pioglitazone Repaglinide Tolbutamide | ↔ Glimepiride (CYP2C9) ↔ Glipizide (CYP2C9) ↔ Glyburide (CYP2C9) ↕ Pioglitazone (CYP2C8 and CYP3A4) ↕ Repaglinide (CYP2C8 and CYP3A4) ↔ Tolbutamide (CYP2C9)
 | The effect of TPV/ritonavir on CYP2C8 substrate is not known.
Immunosuppressants:
 | Combination with APTIVUS/ritonavir not studied. Cannot predict effect of TPV/ritonavir on immunosuppressants due to conflicting effect of TPV/ritonavir on CYP3A and P-gp. | Increased frequency of monitoring of plasma levels of immunosuppressant drugs is recommended.
Cyclosporine Sirolimus Tacrolimus | ↕ Cyclosporine ↕ Sirolimus ↕ Tacrolimus
Inhaled beta agonist: |  | Concurrent administration of APTIVUS/ritonavir is not recommended. The combination may result in increased risk of cardiovascular adverse events associated with salmeterol, including QT prolongation, palpitations, and sinus tachycardia.
Salmeterol | ↑ Salmeterol | Concurrent administration of APTIVUS/ritonavir is not recommended. The combination may result in increased risk of cardiovascular adverse events associated with salmeterol, including QT prolongation, palpitations, and sinus tachycardia.
Inhaled/Nasal Steroids:
Fluticasone | ↑ Fluticasone | Concomitant use of fluticasone propionate and APTIVUS/ritonavir may increase plasma concentrations of fluticasone propionate, resulting in significantly reduced serum cortisol concentrations. Co-administration of fluticasone propionate and APTIVUS/ritonavir is not recommended unless the potential benefit to the patient outweighs the risk of systemic corticosteroid side effects.
Narcotic Analgesics:
 | Combinations with APTIVUS/ritonavir not studied | Dosage increase and long-term use of meperidine are not recommended due to increased concentrations of the metabolite normeperidine which has both analgesic activity and CNS stimulant activity (e.g., seizures).
Meperidine | ↓ Meperidine, ↑ Normeperidine | Dosage increase and long-term use of meperidine are not recommended due to increased concentrations of the metabolite normeperidine which has both analgesic activity and CNS stimulant activity (e.g., seizures).
Methadone | ↓ Methadone | Dosage of methadone may need to be increased when co-administered with APTIVUS and 200 mg of ritonavir.
 | ↓ S-Methadone, ↓ R-Methadone
Oral Contraceptives/Estrogens:
Ethinyl estradiol | ↓ Ethinyl estradiol concentrations by 50% | Alternative methods of nonhormonal contraception should be used when estrogen based oral contraceptives are co-administered with APTIVUS and 200 mg of ritonavir. Patients using estrogens as hormone replacement therapy should be clinically monitored for signs of estrogen deficiency. Women using estrogens may have an increased risk of non-serious rash.
Proton Pump Inhibitors:
Omeprazole | ↓ Omeprazole, ↔ Tipranavir | Dosage of omeprazole may need to be increased when co-administered with APTIVUS and ritonavir.
PDE-5 Inhibitors:
 | Only the combination of tadalafil with APTIVUS/ritonavir has been studied (at doses used for treatment of erectile dysfunction). | Co-administration with APTIVUS/ritonavir may result in an increase in PDE-5 inhibitor-associated adverse events, including hypotension, syncope, visual disturbances, and priapism.
Sildenafil Tadalafil Vardenafil | ↑ Sildenafil (not studied) ↑ Tadalafil with first dose APTIVUS/ritonavir ↔ Tadalafil at APTIVUS/ritonavir steady-state ↑ Vardenafil (not studied) | Use of PDE-5 inhibitors for pulmonary arterial hypertension (PAH):; - Use of sildenafil (Revatio) is contraindicated when used for the treatment of pulmonary arterial hypertension (PAH) [see Contraindications (4)]. - The following dose adjustments are recommended for use of tadalafil (Adcirca) with APTIVUS/ritonavir:
Sildenafil Tadalafil Vardenafil |  | Co-administration of tadalafil (Adcirca) in patients on APTIVUS/ritonavir:
 |  | In patients receiving APTIVUS/ritonavir for at least one week, start Adcirca at 20 mg once daily. Increase to 40 mg once daily based upon individual tolerability.
 |  | Co-administration of APTIVUS/ritonavir in patients on tadalafil (Adcirca):
 |  | Avoid use of tadalafil (Adcirca) during the initiation of APTIVUS/ritonavir. Stop Adcirca at least 24 hours prior to starting APTIVUS/ritonavir. After at least one week following the initiation of APTIVUS/ritonavir, resume Adcirca at 20 mg once daily. Increase to 40 mg once daily based upon individual tolerability.
 |  | Use of PDE-5 inhibitors for erectile dysfunction:
 |  | Concomitant use of PDE-5 inhibitors with APTIVUS/ritonavir should be used with caution and in no case should the starting dose of:; - sildenafil exceed 25 mg within 48 hours - tadalafil exceed 10 mg every 72 hours - vardenafil exceed 2.5 mg every 72 hours
 |  | Use with increased monitoring for adverse events.
Oral Anticoagulants:
Warfarin | ↔ S-Warfarin | Frequent INR (international normalized ratio) monitoring upon initiation of APTIVUS/ritonavir therapy.
↑ increase, ↓ decrease, ↔ no change, ↕ unable to predict

8 USE IN SPECIFIC POPULATIONS

8.1 Pregnancy

Pregnancy Exposure Registry

There is a pregnancy exposure registry that monitors pregnancy outcomes in women exposed to APTIVUS during pregnancy. Healthcare providers are encouraged to register patients by calling the Antiretroviral Pregnancy Registry (APR) at 1-800-258-4263.

Risk Summary

Prospective pregnancy data from the APR and an Expanded Access program are not sufficient to adequately assess the risk of major birth defects, miscarriage, or adverse maternal or fetal outcomes. Tipranavir use during pregnancy has been evaluated in a limited number of women as reported by the APR and an Expanded Access program, and available data show no birth defects in 13 first trimester exposures (see Data) compared with the background rate for major birth defects of 2.7% in the US reference population of the Metropolitan Atlanta Congenital Defects Program (MACDP). The rate of miscarriage is not reported in the APR. The estimated background rate of miscarriage in clinically recognized pregnancies in the U.S. general population is 15-20%. The background risk of birth defects and miscarriage for the indicated population is unknown. Methodological limitations of the APR include the use of MACDP as the external comparator group. The MACDP population is not disease-specific, evaluates women and infants from a limited geographic area, and does not include outcomes for births that occurred at <20 weeks gestation.

In animal reproduction studies, fetal toxicities were observed with tipranavir at maternally toxic doses with systemic exposures (AUC) less than those in humans at the recommended human dose (RHD) (see Data).

Data

Human Data

Based on prospective reports to the APR and an Expanded Access program for approximately 17 live births following exposure to tipranavir-containing regimens (including 13 live births exposed in the first trimester and 4 live births exposed in the second/third trimester), there were no birth defects reported in live-born infants.

Tipranavir has been shown to cross the placenta.

Animal Data

Tipranavir was administered orally to pregnant rats (at 0, 40, 400, or 1000 mg/kg/day from gestation day 6 to 17) and rabbits (at 0, 75, 150, or 375 mg/kg/day from gestation day 6 to 20). In rats, fetal toxicities including decreased body weight and sternebrae ossification occurred at maternally toxic doses (≥400 mg/kg/day) (approximately 0.8 times human exposure at the RHD). In rabbits, fetal toxicities including decreased fetal body weights, wavy ribs, and bent femurs occurred at a maternally toxic dose (375 mg/kg/day) (approximately 0.05 times human exposure at the RHD). Maternal toxicity included an increased incidence of abortions at doses ≥150 mg/kg/day (approximately 0.05 times human exposure at the RHD).

In the pre/post-natal development study, tipranavir was administered orally to rats at 0, 40, 400, 1000 mg/kg/day from gestation day 6 to lactation day 21. The only significant effect observed was growth inhibition of the offspring at maternally toxic doses (≥400 mg/kg/day) (approximately 0.8 times human exposure at the RHD).

8.2 Lactation

Risk Summary

There is no information regarding the presence of tipranavir in human milk, the effects on the breastfed infant, or the effects on milk production. Tipranavir is present in rat milk (see Data). Potential risks of breastfeeding include: (1) HIV-1 transmission (in HIV-1 negative infants), (2) developing viral resistance (in HIV-1-positive patients), and (3) adverse reactions in a breastfed infant similar to those seen in adults.

Data

In a lactation study, tipranavir was excreted into the milk of lactating rats following a single oral dose of tipranavir (10 mg/kg) on lactation/postpartum day 14, with a maximal milk concentration achieved 2 hours post-administration (milk concentration 0.13 times that of maternal plasma concentration).

8.3 Females and Males of Reproductive Potential

Contraception

Use of APTIVUS may reduce the efficacy of estrogen-based oral contraceptives. Advise patients to use alternative methods of nonhormonal contraception [see Drug Interactions (7.2)].

8.4 Pediatric Use

The safety and effectiveness of APTIVUS, co-administered with ritonavir have been established in pediatric patients for combination antiretroviral treatment of HIV-1 infected pediatric patients weighing 36 kg or higher who are treatment-experienced and infected with HIV-1 strains resistant to more than one protease inhibitor (PI) [see Indications and Usage (1) and Dosage and Administration (2.2)].

The safety, pharmacokinetic profile, and virologic and immunologic responses of APTIVUS in those weighing 36 kg or higher were similar to those observed in adults. However, rash was reported more frequently in pediatric subjects than in adults [see Warnings and Precautions (5.6), Adverse Reactions (6.2), Clinical Pharmacology (12.3), and Clinical Studies (14.2)].

The safety and effectiveness of APTIVUS, co-administered with ritonavir have been established in pediatric patients greater than 2 years of age or weighing less than 36 kg, but not recommended due to lack of a suitable pediatric formulation.

8.5 Geriatric Use

Clinical studies of APTIVUS/ritonavir did not include sufficient numbers of subjects aged 65 and over to determine whether they respond differently than younger subjects. In general, caution should be exercised in the administration and monitoring of APTIVUS in elderly patients reflecting the greater frequency of decreased hepatic, renal, or cardiac function, and of concomitant disease or other drug therapy.

8.6 Hepatic Impairment

Tipranavir is principally metabolized by the liver. Caution should be exercised when administering APTIVUS/ritonavir to patients with mild (Child-Pugh Class A) hepatic impairment because tipranavir concentrations may be increased [see Clinical Pharmacology (12.3)]. APTIVUS/ritonavir is contraindicated in patients with moderate or severe (Child-Pugh Class B or Child-Pugh Class C) hepatic impairment [see Contraindications (4)].

10 OVERDOSAGE

There is no known antidote for APTIVUS overdose. Treatment of overdose should consist of general supportive measures, including monitoring of vital signs and observation of the patient's clinical status. If indicated, elimination of unabsorbed tipranavir should be achieved by emesis or gastric lavage. Administration of activated charcoal may also be used to aid in removal of unabsorbed drug. Since tipranavir is highly protein bound, dialysis is unlikely to provide significant removal of the drug.

11 DESCRIPTION

APTIVUS is a protease inhibitor of HIV-1 belonging to the class of 4-hydroxy-5,6-dihydro-2-pyrone sulfonamides.

The chemical name of tipranavir is 2-Pyridinesulfonamide, N-[3-[(1R)-1-[(6R)-5,6-dihydro-4-hydroxy-2-oxo-6-(2-phenylethyl)-6-propyl-2H-pyran-3-yl]propyl]phenyl]-5-(trifluoromethyl). It has a molecular formula of C31H33F3N2O5S and a molecular weight of 602.7. Tipranavir has the following structural formula and is a single stereoisomer with the 1R, 6R configuration.

Tipranavir is a white to off-white to slightly yellow solid. It is freely soluble in dehydrated alcohol and propylene glycol, and insoluble in aqueous buffer at pH 7.5.

APTIVUS soft gelatin capsules are for oral administration. Each capsule contains 250 mg tipranavir. The major inactive ingredients in the capsule are dehydrated alcohol (7% w/w or 0.1 g per capsule), polyoxyl 35 castor oil, propylene glycol, mono/diglycerides of caprylic/capric acid and gelatin.

12 CLINICAL PHARMACOLOGY

12.1 Mechanism of Action

Tipranavir is an antiretroviral drug [see Microbiology (12.4)].

12.2 Pharmacodynamics

ECG Evaluation

The effect of APTIVUS/ritonavir on the QTcF interval was measured in a study in which 81 healthy subjects received the following treatments twice daily for 2.5 days: APTIVUS/ritonavir (500 mg/200 mg), APTIVUS/ritonavir at a supra-therapeutic dose (750 mg/200 mg), and placebo/ritonavir (-/200 mg). After baseline and placebo adjustment, the maximum mean QTcF change was 3.2 ms (1-sided 95% Upper CI: 5.6 ms) for the 500 mg/200 mg dose and 8.3 ms (1-sided 95% Upper CI: 10.9 ms) for the supra-therapeutic 750 mg/200 mg dose.

Antiviral Activity in vivo

The median Inhibitory Quotient (IQ) determined from 264 treatment-experienced adult subjects was about 80 (inter-quartile range: 31-226), from the controlled clinical trials 1182.12 and 1182.48. The IQ is defined as the tipranavir trough concentration divided by the viral EC50 value, corrected for protein binding. There was a relationship between the proportion of subjects with a ≥1 log10 reduction of viral load from baseline at week 48 and their IQ value. Among the 198 subjects receiving APTIVUS/ritonavir with no new enfuvirtide use (e.g., new enfuvirtide, defined as initiation of enfuvirtide for the first time), the response rate was 23% in those with an IQ value <80 and 59% in those with an IQ value ≥80. Among the 66 subjects receiving APTIVUS/ritonavir with new enfuvirtide, the response rates in subjects with an IQ value <80 versus those with an IQ value ≥80 were 55% and 71%, respectively. These IQ groups are derived from a select population and are not meant to represent clinical breakpoints.

12.3 Pharmacokinetics

In order to achieve effective tipranavir plasma concentrations and a twice-daily dosing regimen, co-administration of APTIVUS with ritonavir is essential [see Dosage and Administration (2)]. Ritonavir inhibits hepatic cytochrome P450 3A (CYP3A), the intestinal P-gp efflux pump and possibly intestinal CYP3A. In a dose-ranging evaluation in 113 HIV-1 negative male and female volunteers, there was a 29-fold increase in the geometric mean morning steady-state trough plasma concentrations of tipranavir following APTIVUS co-administered with low-dose ritonavir (500 mg/200 mg twice daily) compared to APTIVUS 500 mg twice daily without ritonavir. In adults the mean systemic ritonavir concentration when 200 mg of ritonavir was given with 500 mg of APTIVUS was similar to the concentrations observed when 100 mg was given with the other protease inhibitors.

Figure 1 displays mean plasma concentrations of tipranavir and ritonavir at steady state for 30 HIV-1 infected adult subjects dosed with 500 mg/200 mg tipranavir/ritonavir for 14 days.

Figure 1 Mean Steady State Tipranavir Plasma Concentrations (95% CI) with Ritonavir Co-administration (tipranavir/ritonavir 500 mg/200 mg BID)

Absorption and Bioavailability

Absorption of tipranavir in humans is limited, although no absolute quantification of absorption is available. Tipranavir is a P-gp substrate, a weak P-gp inhibitor, and appears to be a potent P-gp inducer as well. In vivo data suggest that tipranavir/ritonavir, at the dose of 500 mg/200 mg, is a P-gp inhibitor after the first dose and induction of P-gp occurs over time. Tipranavir trough concentrations at steady-state are about 70% lower than those on Day 1, presumably due to intestinal P-gp induction. Steady state is attained in most subjects after 7-10 days of dosing.

Dosing APTIVUS 500 mg with 200 mg ritonavir capsules twice daily for greater than 2 weeks and without meal restriction produced the pharmacokinetic parameters for male and female HIV-1 positive subjects presented in Table 5.

Table 5 Pharmacokinetic Parametersa of tipranavir/ritonavir 500 mg/200 mg for HIV-1 Positive Subjects by Gender
Parameter | Females (n=14) | Males (n=106)
Cptrough (µM) | 41.6 ± 24.3 | 35.6 ± 16.7
Cmax (µM) | 94.8 ± 22.8 | 77.6 ± 16.6
Tmax (h) | 2.9 | 3.0
AUC0-12h (µM∙h) | 851 ± 309 | 710 ± 207
CL (L/h) | 1.15 | 1.27
V (L) | 7.7 | 10.2
t1/2 (h) | 5.5 | 6.0
aPopulation pharmacokinetic parameters reported as mean ± standard deviation

Effects of Food on Oral Absorption

For APTIVUS capsules co-administered with ritonavir capsules at steady-state, no clinically significant changes in tipranavir Cmax, Cp12h, and AUC were observed under fed conditions (500-682 Kcal, 23-25% calories from fat) compared to fasted conditions [see Dosage and Administration (2)]. The effect of food on tipranavir exposure when APTIVUS capsules is co-administered with ritonavir tablets has not been evaluated [see Dosage and Administration (2)]. For information on the effect of food on the bioavailability of ritonavir tablets, please refer to the ritonavir tablet prescribing information.

Distribution

Tipranavir is extensively bound to plasma proteins (>99.9%). It binds to both human serum albumin and α-1-acid glycoprotein. The mean fraction of tipranavir (dosed without ritonavir) unbound in plasma was similar in clinical samples from healthy volunteers and HIV-1 positive subjects. Total plasma tipranavir concentrations for these samples ranged from 9 to 82 µM. The unbound fraction of tipranavir appeared to be independent of total drug concentration over this concentration range.

No studies have been conducted to determine the distribution of tipranavir into human cerebrospinal fluid or semen.

Metabolism

In vitro metabolism studies with human liver microsomes indicated that CYP3A4 is the predominant CYP enzyme involved in tipranavir metabolism.

The oral clearance of tipranavir decreased after the addition of ritonavir, which may represent diminished first-pass clearance of the drug at the gastrointestinal tract as well as the liver.

The metabolism of tipranavir in the presence of 200 mg ritonavir is minimal. Administration of ^14C-tipranavir to subjects that received APTIVUS/ritonavir 500 mg/200 mg dosed to steady-state demonstrated that unchanged tipranavir accounted for 98.4% or greater of the total plasma radioactivity circulating at 3, 8, or 12 hours after dosing. Only a few metabolites were found in plasma, and all were at trace levels (0.2% or less of the plasma radioactivity). In feces, unchanged tipranavir represented the majority of fecal radioactivity (79.9% of fecal radioactivity). The most abundant fecal metabolite, at 4.9% of fecal radioactivity (3.2% of dose), was a hydroxyl metabolite of tipranavir. In urine, unchanged tipranavir was found in trace amounts (0.5% of urine radioactivity). The most abundant urinary metabolite, at 11.0% of urine radioactivity (0.5% of dose) was a glucuronide conjugate of tipranavir.

Elimination

Administration of ^14C-tipranavir to subjects (n=8) that received APTIVUS/ritonavir 500 mg/200 mg dosed to steady-state demonstrated that most radioactivity (median 82.3%) was excreted in feces, while only a median of 4.4% of the radioactive dose administered was recovered in urine. In addition, most radioactivity (56%) was excreted between 24 and 96 hours after dosing. The effective mean elimination half-life of tipranavir/ritonavir in healthy volunteers (n=67) and HIV-1 infected adult subjects (n=120) was approximately 4.8 and 6.0 hours, respectively, at steady state following a dose of 500 mg/200 mg twice daily with a light meal.

Special Populations

Renal Impairment

APTIVUS pharmacokinetics has not been studied in patients with renal dysfunction. However, since the renal clearance of tipranavir is negligible, a decrease in total body clearance is not expected in patients with renal insufficiency.

Hepatic Impairment

In a study comparing 9 HIV-1 negative subjects with mild (Child-Pugh Class A) hepatic impairment to 9 HIV-1 negative controls, the single and multiple dose plasma concentrations of tipranavir and ritonavir were increased in subjects with hepatic impairment, but were within the range observed in clinical trials. No dosing adjustment is required in patients with mild hepatic impairment.

The influence of moderate hepatic impairment (Child-Pugh Class B) or severe hepatic impairment (Child-Pugh Class C) on the multiple-dose pharmacokinetics of tipranavir administered with ritonavir has not been evaluated [see Dosage and Administration (2), Contraindications (4), and Warnings and Precautions (5.2)].

Gender

Evaluation of steady-state plasma tipranavir trough concentrations at 10-14 h after dosing from the controlled clinical trials 1182.12 and 1182.48 demonstrated that females generally had higher tipranavir concentrations than males. After 4 weeks of APTIVUS/ritonavir 500 mg/200 mg BID, the median plasma trough concentration of tipranavir was 43.9 µM for females and 31.1 µM for males. The difference in concentrations does not warrant a dose adjustment.

Race

Evaluation of steady-state plasma tipranavir trough concentrations at 10-14 h after dosing from the controlled clinical trials 1182.12 and 1182.48 demonstrated that white males generally had more variability in tipranavir concentrations than black males, but the median concentration and the range making up the majority of the data are comparable between the races.

Geriatric Patients

Evaluation of steady-state plasma tipranavir trough concentrations at 10-14 h after dosing from the controlled clinical trials 1182.12 and 1182.48 demonstrated that there was no change in median trough tipranavir concentrations as age increased for either gender through 65 years of age. There were an insufficient number of women greater than age 65 years in the two trials to evaluate the elderly.

Pediatric Patients

Among pediatric subjects in clinical trial 1182.14, steady-state plasma tipranavir trough concentrations were obtained 10 to 14 hours following study drug administration. The exposure differences between pediatric subjects and adults are not considered to be clinically significant based on the activity and safety data.

Drug Interactions

Drug interaction studies were performed with APTIVUS capsules co-administered with ritonavir, and other drugs likely to be co-administered and some drugs commonly used as probes for pharmacokinetic interactions. The effects of co-administration of APTIVUS with 200 mg ritonavir on the AUC, Cmax, and Cmin of tipranavir or the co-administered drug, are summarized in Tables 6 and 7, respectively. For information regarding clinical recommendations see Drug Interactions (7.2).

Table 6 Drug Interactions: Pharmacokinetic Parameters for Tipranavir in the Presence of Co-administered Drugs
Co-administered Drug | Co-administered Drug Dose (Schedule) | tipranavir/ ritonavir Drug Dose (Schedule) | n | PK | Ratio (90% Confidence Interval) of Tipranavir Pharmacokinetic Parameters with/without Co-administered Drug; No Effect = 1.00
Co-administered Drug | Co-administered Drug Dose (Schedule) | tipranavir/ ritonavir Drug Dose (Schedule) | n | PK | Cmax | AUC | Cmin
Antacids (Maalox®) | 20 mL (1 dose) | 500 mg/200 mg (1 dose) | 23 | ↓ | 0.75 (0.63, 0.88) | 0.73 (0.64, 0.84) | -
Atazanavir/ritonavir | 300 mg/100 mg QD (9 doses) | 500 mg/100 mg BID (34 doses) | 13 | ↑ | 1.08 (0.98, 1.20) | 1.20 (1.09, 1.32) | 1.75 (1.39, 2.20)
Atorvastatin | 10 mg (1 dose) | 500 mg/200 mg BID (14 doses) | 22 | ↔ | 0.96 (0.86, 1.07) | 1.08 (1.00, 1.15) | 1.04 (0.89, 1.22)
Clarithromycin | 500 mg BID (25 doses) | 500 mg/200 mg BID* | 24 (68) | ↑ | 1.40 (1.24, 1.47) | 1.66 (1.43, 1.73) | 2.00 (1.58, 2.47)
Didanosine | 400 mg (1 dose) | 500 mg/100 mg BID (27 doses) | 5 | ↓ | 1.32 (1.09, 1.60) | 1.08 (0.82, 1.42) | 0.66 (0.31, 1.43)
Efavirenz | 600 mg QD (8 doses) | 500 mg/100 mg BID* | 21 (89) | ↓ | 0.79 (0.69, 0.89) | 0.69 (0.57, 0.83) | 0.58 (0.36, 0.86)
Efavirenz |  | 750 mg/200 mg BID* | 25 (100) | ↔ | 0.97 (0.85, 1.09) | 1.01 (0.85, 1.18) | 0.97 (0.69, 1.28)
Ethinyl estradiol /Norethindrone | 0.035 mg/1.0 mg (1 dose) | 500 mg/100 mg BID (21 doses) | 21 | ↓ | 1.10 (0.98, 1.24) | 0.98 (0.88, 1.11) | 0.73 (0.59, 0.90)
Ethinyl estradiol /Norethindrone |  | 750 mg/200 mg BID (21 doses) | 13 | ↔ | 1.01 (0.96, 1.06) | 0.98 (0.90, 1.07) | 0.91 (0.69, 1.20)
Fluconazole | 100 mg QD (12 doses) | 500 mg/200 mg BID* | 20 (68) | ↑ | 1.32 (1.18, 1.47) | 1.50 (1.29, 1.73) | 1.69 (1.33, 2.09)
Loperamide | 16 mg (1 dose) | 750 mg/200 mg BID (21 doses) | 24 | ↓ | 1.03 (0.92, 1.17) | 0.98 (0.86, 1.12) | 0.74 (0.62, 0.88)
Rifabutin | 150 mg (1 dose) | 500 mg/200 mg BID (15 doses) | 21 | ↔ | 0.99 (0.93, 1.07) | 1.00 (0.96, 1.04) | 1.16 (1.07, 1.27)
Rosuvastatin | 10 mg (1 dose) | 500 mg/200 mg BID (24 doses) | 16 | ↔ | 1.08 (1.00, 1.17) | 1.06 (0.97, 1.15) | 0.99 (0.88, 1.11)
Tadalafil | 10 mg (1 dose) | 500 mg/200 mg BID (17 doses) | 17 | ↔ | 0.90 (0.80, 1.01) | 0.85 (0.74, 0.97) | 0.81 (0.70, 0.94)
Tenofovir | 300 mg (1 dose) | 500 mg/100 mg BID | 22 | ↓ | 0.83 (0.74, 0.94) | 0.82 (0.75, 0.91) | 0.79 (0.70, 0.90)
Tenofovir |  | 750 mg/200 mg BID (23 doses) | 20 | ↔ | 0.89 (0.84, 0.96) | 0.91 (0.85, 0.97) | 0.88 (0.78, 1.00)
Valacyclovir | 500 mg (1 dose) | 500 mg/200 mg BID (23 doses) | 26 | ↔ | 1.02 (0.95, 1.10) | 1.01 (0.96, 1.06) | 0.98 (0.93, 1.04)
Zidovudine | 300 mg (1 dose) | 500 mg/100 mg BID | 29 | ↓ | 0.87 (0.80, 0.94) | 0.82 (0.76, 0.89) | 0.77 (0.68, 0.87)
Zidovudine |  | 750 mg/200 mg BID (23 doses) | 25 | ↔ | 1.02 (0.94, 1.10) | 1.02 (0.92, 1.13) | 1.07 (0.86, 1.34)
*steady state comparison to historical data (n)
↑ increase, ↓ decrease, ↔ no change, ↕ unable to predict

Table 7 Drug Interactions: Pharmacokinetic Parameters for Co-administered Drug in the Presence of APTIVUS/ritonavir
Co-administered Drug | Co-administered Drug Dose (Schedule) | tipranavir/ ritonavir Drug Dose (Schedule) | n | PK | Ratio (90% Confidence Interval) of Co-administered Drug Pharmacokinetic Parameters with/without tipranavir/ritonavir; No Effect = 1.00
Co-administered Drug | Co-administered Drug Dose (Schedule) | tipranavir/ ritonavir Drug Dose (Schedule) | n | PK | Cmax | AUC | Cmin
Abacavira | 300 mg BID (43 doses) | 250 mg/200 mg BID 750 mg/100 mg BID 1250 mg/100 mg BID (42 doses) | 28 14 11 | ↓ ↓ ↓ | 0.56 (0.48, 0.66) 0.54 (0.47, 0.63) 0.48 (0.42, 0.53) | 0.56 (0.49, 0.63) 0.64 (0.55, 0.74) 0.65 (0.55, 0.76) | - - -
Acyclovirh | 500 mg (1 dose) | 500 mg/200 mg BID (23 doses) | 26 | ↔ | 0.95 (0.88, 1.02) | 1.07 (1.04, 1.09) | -
Amprenavir/ritonavira | 600 mg/100 mg BID (27 doses) | 500 mg/200 mg BID (28 doses) | 16 74 | ↓ ↓ | 0.61 (0.51, 0.73)e | 0.56 (0.49, 0.64)e - | 0.45 (0.38, 0.53)e 0.44 (0.39, 0.49)f
Atazanavir/ritonavir | 300 mg/100 mg QD (9 doses) | 500 mg/100 mg BID (34 doses) | 13 | ↓ | 0.43 (0.38, 0.50) | 0.32 (0.29, 0.36) | 0.19 (0.15, 0.24)
Atorvastatin | 10 mg (1 dose) | 500 mg/200 mg BID (17 doses) | 22 | ↑ | 8.61 (7.25, 10.21) | 9.36 (8.02, 10.94) | 5.19 (4.21, 6.40)
Orthohydroxy-atorvastatin Parahydroxy-atorvastatin |  |  | 21, 12, 17 | ↓ | 0.02 (0.02, 0.03) | 0.11 (0.08, 0.17) | 0.07 (0.06, 0.08)
Orthohydroxy-atorvastatin Parahydroxy-atorvastatin |  |  | 13, 22, 1 | ↓ | 1.04 (0.87, 1.25) | 0.18 (0.14, 0.24) | 0.33 (NA)
Buprenorphine/Naloxoneb | 16 mg/4 mg 24 mg/6 mg (daily) | 500 mg/200 mg BID (16 doses)
Buprenorphine |  |  | 10 | ↔ | 0.86 (0.68, 1.10) | 0.99 (0.80, 1.23) | 0.94 (0.74, 1.19)
Carbamazepine | 100 mg BID (29 doses) | 500 mg/200 mg (1 dose) | 7 | ↔ | 1.04 (1.00, 1.07) | 1.05 (1.02, 1.09) | 1.17 (1.11, 1.24)
Carbamazepine | (43 doses) | (15 doses) | 7 | ↔ | 1.10 (0.85, 1.42) | 1.08 (0.91, 1.27) | 1.07 (0.90, 1.27)
Carbamazepine | 200 mg BID (29 doses) | 500 mg/200 mg (1 dose) | 17 | ↔ | 1.00 (0.96, 1.04) | 1.04 (1.00, 1.08) | 1.16 (1.11, 1.22)
Carbamazepine | (43 doses) | (15 doses) | 17 | ↑ | 1.22 (1.11, 1.34) | 1.26 (1.15, 1.38) | 1.35 (1.22, 1.50)
Clarithromycin | 500 mg BID (25 doses) | 500 mg/200 mg BID (15 doses) | 21 | ↑ | 0.95 (0.83, 1.09) | 1.19 (1.04, 1.37) | 1.68 (1.42, 1.98)
14-OH-clarithromycin |  |  | 21 | ↓ | 0.03 (0.02, 0.04) | 0.03 (0.02, 0.04) | 0.05 (0.04, 0.07)
Didanosinec | 200 mg BID, ≥60 kg 125 mg BID, <60 kg (43 doses) | 250 mg/200 mg BID 750 mg/100 mg BID 1250 mg/100 mg BID (42 doses) | 10 8 9 | ↓ ↔ ↔ | 0.57 (0.42, 0.79) 0.76 (0.49, 1.17) 0.77 (0.47, 1.26) | 0.67 (0.51, 0.88) 0.97 (0.64, 1.47) 0.87 (0.47, 1.65) | - - -
Didanosinec | 400 mg (1 dose) | 500 mg/100 mg BID (27 doses) | 5 | ↔ | 0.80 (0.63, 1.02) | 0.90 (0.72, 1.11) | 1.17 (0.62, 2.20)
Dolutegravir | 50 mg QD | 500 mg/200 mg BID | 14 | ↓ | 0.54 (0.50-0.57) | 0.41 (0.38-0.44) | 0.24 (0.21-0.27)
Efavirenzc | 600 mg QD (15 doses) | 500 mg/100 mg BID 750 mg/200 mg BID (15 doses) | 24 22 | ↔ ↔ | 1.09 (0.99, 1.19) 1.12 (0.98, 1.28) | 1.04 (0.97, 1.12) 1.00 (0.93, 1.09) | 1.02 (0.92, 1.12) 0.94 (0.84, 1.04)
Ethinyl estradiol | 0.035 mg (1 dose) | 500 mg/100 mg BID 750 mg/200 mg BID (21 doses) | 21 13 | ↓ ↓ | 0.52 (0.47, 0.57) 0.48 (0.42, 0.57) | 0.52 (0.48, 0.56) 0.57 (0.54, 0.60) | - -
Fluconazole | 200 mg (Day 1) then 100 mg QD (6 or 12 doses) | 500 mg/200 mg BID (2 or 14 doses) | 19 19 | ↔ ↔ | 0.97 (0.94, 1.01) 0.94 (0.91, 0.98) | 0.99 (0.97, 1.02) 0.92 (0.88, 0.95) | 0.98 (0.94, 1.02) 0.89 (0.85, 0.92)
Lopinavir/ritonavira | 400 mg/100 mg BID (27 doses) | 500 mg/200 mg BID (28 doses) | 21 69 | ↓ ↓ | 0.53 (0.40, 0.69)e - | 0.45 (0.32, 0.63)e - | 0.30 (0.17, 0.51)e 0.48 (0.40, 0.58)f
Loperamide | 16 mg (1 dose) | 750 mg/200 mg BID (21 doses) | 24 | ↓ | 0.39 (0.31, 0.48) | 0.49 (0.40, 0.61) | -
N-Demethyl-Loperamide |  |  | 24 | ↓ | 0.21 (0.17, 0.25) | 0.23 (0.19, 0.27) | -
Lamivudinea | 150 mg BID (43 doses) | 250 mg/200 mg BID 750 mg/100 mg BID 1250 mg/100 mg BID (42 doses) | 64 46 35 | ↔ ↔ ↔ | 0.96 (0.89, 1.03) 0.86 (0.78, 0.94) 0.71 (0.62, 0.81) | 0.95 (0.89, 1.02) 0.96 (0.90, 1.03) 0.82 (0.66, 1.00) | - - -
Methadone | 5 mg (1 dose) | 500 mg/200 mg BID (16 doses) | 14 | ↓ | 0.45 (0.41, 0.49) | 0.47 (0.44, 0.51) | 0.50 (0.46, 0.54)
R-methadone |  |  |  |  | 0.54 (0.50, 0.58) | 0.52 (0.49, 0.56) | -
S-methadone |  |  |  |  | 0.38 (0.35, 0.43) | 0.37 (0.34, 0.41) | -
Nevirapinea | 200 mg BID (43 doses) | 250 mg/200 mg BID 750 mg/100 mg BID 1250 mg/100 mg BID (42 doses) | 26 22 17 | ↔ ↔ ↔ | 0.97 (0.90, 1.04) 0.86 (0.76, 0.97) 0.71 (0.62, 0.82) | 0.97 (0.91, 1.04) 0.89 (0.78, 1.01) 0.76 (0.63, 0.91) | 0.96 (0.87, 1.05) 0.93 (0.80, 1.08) 0.77 (0.64, 0.92)
Norethindrone | 1.0 mg (1 dose) | 500 mg/100 mg BID 750 mg/200 mg BID (21 doses) | 21 13 | ↔ ↔ | 1.03 (0.94, 1.13) 1.08 (0.97, 1.20) | 1.14 (1.06, 1.22) 1.27 (1.13, 1.43) | - -
Raltegravir | 400 mg BID | 500 mg/200 mg BID | 15 | ↓ | 0.82 (0.46, 1.46) | 0.76 (0.49, 1.19) | 0.45 (0.31, 0.66)g
Rifabutin | 150 mg (1 dose) | 500 mg/200 mg BID (15 doses) | 20 | ↑ | 1.70 (1.49, 1.94) | 2.90 (2.59, 3.26) | 2.14 (1.90, 2.41)
25-O-desacetyl-rifabutin |  |  | 20 | ↑ | 3.20 (2.78, 3.68) | 20.71 (17.66, 24.28) | 7.83 (6.70, 9.14)
Rifabutin + 25-O-desacetyl-rifabutind |  |  | 20 | ↑ | 1.86 (1.63, 2.12) | 4.33 (3.86, 4.86) | 2.76 (2.44, 3.12)
Rosuvastatin | 10 mg (1 dose) | 500 mg/200 mg BID (24 doses) | 16 | ↑ | 2.23 (1.83, 2.72) | 1.26 (1.08, 1.46) | 1.06 (0.93, 1.20)
Saquinavir/ritonavira | 600 mg/100 mg BID (27 doses) | 500 mg/200 mg BID (28 doses) | 20 68 | ↓ ↓ | 0.30 (0.23, 0.40)e - | 0.24 (0.19, 0.32)e - | 0.18 (0.13, 0.26)e 0.20 (0.16, 0.25)f
Stavudinea | 40 mg BID ≥60 kg 30 mg BID <60 kg (43 doses) | 250 mg/200 mg BID 750 mg/100 mg BID 1250 mg/100 mg BID (42 doses) | 26 22 19 | ↔ ↔ ↔ | 0.90 (0.81, 1.02) 0.76 (0.66, 0.89) 0.74 (0.69, 0.80) | 1.00 (0.91, 1.11) 0.84 (0.74, 0.96) 0.93 (0.83, 1.05) | - - -
Tadalafil | 10 mg (1 dose) | 500 mg/200 mg (1 dose) | 17 | ↑ | 0.78 (0.72, 0.84) | 2.33 (2.02, 2.69) | -
 | 10 mg (1 dose) | 500 mg/200 mg BID (17 doses) | 17 | ↔ | 0.70 (0.63, 0.78) | 1.01 (0.83, 1.21) | -
Tenofovir | 300 mg (1 dose) | 500 mg/100 mg BID 750 mg/200 mg BID (23 doses) | 22 20 | ↓ ↓ | 0.77 (0.68, 0.87) 0.62 (0.54, 0.71) | 0.98 (0.91, 1.05) 1.02 (0.94, 1.10) | 1.07 (0.98, 1.17) 1.14 (1.01, 1.27)
Zidovudinec | 300 mg BID | 250 mg/200 mg BID | 48 | ↓ | 0.54 (0.47, 0.62) | 0.58 (0.51, 0.66) | -
 | 300 mg BID | 750 mg/100 mg BID | 31 | ↓ | 0.51 (0.44, 0.60) | 0.64 (0.55, 0.75) | -
 | 300 mg BID (43 doses) | 1250 mg/100 mg BID (42 doses) | 23 | ↓ | 0.49 (0.40, 0.59) | 0.69 (0.49, 0.97) | -
 | 300 mg (1 dose) | 500 mg/100 mg BID 750 mg/200 mg BID (23 doses) | 29 25 | ↓ ↔ | 0.39 (0.33, 0.45) 0.44 (0.36, 0.54) | 0.57 (0.52, 0.63) 0.67 (0.62, 0.73) | 0.89 (0.81, 0.99) 1.25 (1.08, 1.44)
Zidovudine glucuronide |  | 500 mg/100 mg BID 750 mg/200 mg BID (23 doses) | 29 25 | ↑ ↑ | 0.82 (0.74, 0.90) 0.82 (0.73, 0.92) | 1.02 (0.97, 1.06) 1.09 (1.05, 1.14) | 1.52 (1.34, 1.71) 1.94 (1.62, 2.31)
a HIV-1 positive subjects
b Buprenorphine/Naloxone maintenance subjects
c HIV-1 positive subjects (tipranavir/ritonavir 250 mg/200 mg, 750 mg/200 mg and 1250 mg/100 mg) and healthy volunteers (tipranavir/ritonavir 500 mg/100 mg and 750 mg/200 mg)
d Normalized sum of parent drug (rifabutin) and active metabolite (25-O-desacetyl-rifabutin)
e Intensive PK analysis
f Drug levels obtained at 8-16 hrs post-dose
g n = 14 for Cmin
hAdministered as Valacyclovir
↑ increase, ↓ decrease, ↔ no change, ↕ unable to predict

12.4 Microbiology

Mechanism of Action

Tipranavir (TPV) is an HIV-1 protease inhibitor that inhibits the virus-specific processing of the viral Gag and Gag-Pol polyproteins in HIV-1 infected cells, thus preventing formation of mature virions.

Antiviral Activity

Tipranavir inhibits the replication of laboratory strains of HIV-1 and clinical isolates in acute models of T-cell infection, with 50% effective concentrations (EC50) ranging from 0.03 to 0.07 µM (18-42 ng/mL). Tipranavir demonstrates antiviral activity in cell culture against a broad panel of HIV-1 group M non-clade B isolates (A, C, D, F, G, H, CRF01 AE, CRF02 AG, CRF12 BF). Group O and HIV-2 isolates have reduced susceptibility in cell culture to tipranavir with EC50 values ranging from 0.164 -1 µM and 0.233-0.522 µM, respectively. The cell culture antiviral activity of tipranavir in combination with the HIV-1 protease inhibitors amprenavir, atazanavir, lopinavir and saquinavir, and with the HIV-1 NRTI lamivudine was additive to antagonistic. No antagonism was seen when combined with the HIV-1 protease inhibitors indinavir, nelfinavir, or ritonavir, with the NNRTIs delavirdine, efavirenz, and nevirapine, with the NRTIs abacavir, didanosine, emtricitabine, stavudine, tenofovir, and zidovudine, or with the gp41 fusion inhibitor enfuvirtide in cell culture. There was no antagonism of the cell culture combinations of tipranavir with either adefovir or ribavirin, used in the treatment of viral hepatitis.

Resistance

In cell culture:

HIV-1 isolates with a decreased susceptibility to tipranavir have been selected in cell culture and obtained from subjects treated with APTIVUS/ritonavir (TPV/ritonavir). After 9 months of culture in TPV-containing medium, HIV-1 isolates with 87-fold reduced susceptibility to tipranavir were selected in cell culture; these contained 10 protease substitutions that developed in the following order: L33F, I84V, K45I, I13V, V32I, V82L, M36I, A71V, L10F, and I54V/T. Changes in the Gag polyprotein CA/P2 cleavage site were also observed following drug selection. Experiments with site-directed mutants of HIV-1 showed that the presence of 6 substitutions in the protease coding sequence (I13V, V32I, L33F, K45I, V82L, I84V) conferred >10-fold reduced susceptibility to tipranavir.

Clinical Trials of Treatment-Experienced Subjects:

In controlled clinical trials 1182.12 and 1182.48, multiple protease inhibitor-resistant HIV-1 isolates from 59 treatment-experienced adult subjects who received APTIVUS/ritonavir and experienced virologic rebound developed amino acid substitutions that were associated with resistance to tipranavir. The most common amino acid substitutions that developed on 500 mg/200 mg APTIVUS/ritonavir in greater than 20% of APTIVUS/ritonavir virologic failure isolates were L33V/I/F, V82T, and I84V. Other substitutions that developed in 10 to 20% of APTIVUS/ritonavir virologic failure isolates included L10V/I/S, I13V, E35D/G/N, I47V, I54A/M/V, K55R, V82L, and L89V/M. Evolution at protease gag polyprotein cleavage sites was also observed. Among 28 pediatric subjects in clinical trial 1182.14 who experienced virologic failure or non-response, the emergent protease amino acid codon substitutions were similar to those observed in adult virologic failure isolates.

In clinical trials 1182.12 and 1182.48 tipranavir resistance was detected at virologic rebound after an average of 38 weeks of APTIVUS/ritonavir treatment with a median 14-fold decrease in tipranavir susceptibility. Similarly, reduced tipranavir susceptibility was associated with emergent substitutions in pediatric subject isolates.

Cross-resistance

Cross-resistance among protease inhibitors has been observed. Tipranavir had <4-fold decreased susceptibility against 90% (94/105) of HIV-1 clinical isolates resistant to amprenavir, atazanavir, indinavir, lopinavir, nelfinavir, ritonavir, or saquinavir. Tipranavir-resistant viruses which emerged in cell culture from wild-type HIV-1 had decreased susceptibility to the protease inhibitors amprenavir, atazanavir, indinavir, lopinavir, nelfinavir and ritonavir but remained sensitive to saquinavir.

Baseline Genotype and Virologic Outcome Analyses

Genotypic and/or phenotypic analysis of baseline virus may aid in determining tipranavir susceptibility before initiation of APTIVUS/ritonavir therapy. Several analyses were conducted to evaluate the impact of specific substitutions and combination of substitutions on virologic outcome. Both the type and number of baseline protease inhibitor substitutions as well as use of additional active agents (e.g., enfuvirtide) affected APTIVUS/ritonavir response rates in controlled clinical trials 1182.12 and 1182.48 through Week 48 of treatment.

Regression analyses of baseline and/or on-treatment HIV-1 genotypes from 860 treatment-experienced subjects in Phase 2 and 3 trials demonstrated that amino acid substitutions at 16 codons in the HIV-1 protease coding sequence were associated with reduced virologic responses and/or reduced tipranavir susceptibility: L10V, I13V, K20M/R/V, L33F, E35G, M36I, K43T, M46L, I47V, I54A/M/V, Q58E, H69K, T74P, V82L/T, N83D or I84V.

As-treated analyses were also conducted to assess virologic outcome by the number of primary protease inhibitor substitutions present at baseline. Response rates were reduced if five or more protease inhibitor-associated substitutions were present at baseline and subjects did not receive concomitant new enfuvirtide with APTIVUS/ritonavir. See Table 8.

Table 8 Controlled Clinical Trials 1182.12 and 1182.48: Proportion of Responders (confirmed ≥1 log10 decrease at Week 48) by Number of Baseline Primary Protease Inhibitor (PI) Resistance-Associated Substitutions
Number of Baseline Primary PI Substitutionsa | APTIVUS/ritonavir N=578 |  | Comparator PI/ritonavir N=610
Number of Baseline Primary PI Substitutionsa | No New Enfuvirtideb | + New Enfuvirtidec | No New Enfuvirtideb | + New Enfuvirtidec
Overall | 38% (180/470) | 69% (75/108) | 18% (92/524) | 26% (22/86)
1 – 2 | 62% (24/39) | 60% (3/5) | 33% (14/43) | 0% (0/1)
3 – 4 | 48% (96/202) | 71% (27/38) | 23% (45/193) | 38% (13/34)
5+ | 26% (60/229) | 69% (45/65) | 11% (33/288) | 18% (9/51)
aPrimary PI substitutions include any amino acid substitution at positions 30, 32, 36, 46, 47, 48, 50, 53, 54, 82, 84, 88 and 90
bNo new enfuvirtide is defined as recycled or continued use of enfuvirtide or no use of enfuvirtide
cNew enfuvirtide is defined as initiation of enfuvirtide for the first time

The median change from baseline in plasma HIV-1 RNA at weeks 2, 4, 8, 16, 24 and 48 was evaluated by the number of baseline primary protease inhibitor resistance- associated substitutions (1-4 or ≥5) in subjects who received APTIVUS/ritonavir with or without new enfuvirtide. The following observations were made:

- Approximately 1.5 log10 decrease in HIV-1 RNA at early time points (Week 2) regardless of the number of baseline primary protease inhibitor resistance- associated substitutions (1-4 or 5+).
- Subjects with 5 or more primary protease inhibitor resistance-associated substitutions in their HIV-1 at baseline who received APTIVUS/ritonavir without new enfuvirtide (n=303) began to lose their antiviral response after Week 4.
- Early HIV-1 RNA decreases (1.5-2 log10) were sustained through Week 48 in subjects with 5 or more primary protease inhibitor resistance-associated substitutions at baseline who received new enfuvirtide with APTIVUS/ritonavir (n=74).

Baseline Phenotype and Virologic Outcome Analyses

APTIVUS/ritonavir response rates were also assessed by baseline tipranavir phenotype. Relationships between baseline phenotypic susceptibility to tipranavir, substitutions at protease amino acid codons 33, 82, 84 and 90, tipranavir resistance-associated substitutions, and response to APTIVUS/ritonavir therapy at Week-48 are summarized in Tables 9 and 10. These baseline phenotype groups are not meant to represent clinical susceptibility breakpoints for APTIVUS/ritonavir because the data are based on the select 1182.12 and 1182.48 subject population. The data are provided to give clinicians information on the likelihood of virologic success based on pre-treatment susceptibility to APTIVUS/ritonavir in protease inhibitor-experienced subjects.

Table 9 Response by Baseline Tipranavir Phenotype at 48 weeks in the Controlled Clinical Trials 1182.12 and 1182.48
Baseline Tipranavir Phenotype (Fold Change)a | Proportion of Respondersb with No New Enfuvirtidec Use N=211 | Proportion of Respondersb with New Enfuvirtided Use N=68 | Tipranavir Susceptibility
0-3 | 48% (73/153) | 70% (33/47) | Susceptible
>3-10 | 21% (10/48) | 53% (8/15) | Decreased Susceptibility
>10 | 10% (1/10) | 50% (3/6) | Resistant
aChange in tipranavir EC50 value from wild-type reference
bConfirmed ≥1 log10 decrease at Week 48
cNo new enfuvirtide is defined as recycled or continued use of enfuvirtide or no use of enfuvirtide
dNew enfuvirtide is defined as initiation of enfuvirtide for the first time

Table 10 Correlation of Baseline Tipranavir Phenotype to Genotype using HIV-1 isolates from Phase 2 and Phase 3 Clinical Trials
Baseline Tipranavir Phenotype (Fold Change)a | # of Baseline Protease Substitutions at 33, 82, 84, 90 | # of Baseline Tipranavir Resistance-Associated Substitutionsb | Tipranavir Susceptibilityc
0-3 | 0-2 | 0-4 | Susceptible
>3-10 | 3 | 5-7 | Decreased Susceptibility
>10 | 4 | 8+ | Resistant
aChange in tipranavir EC50 value from wild-type reference
bNumber of amino acid substitutions in HIV-1 protease among L10V, I13V, K20M/R/V, L33F, E35G, M36I, K43T, M46L, I47V, I54A/M/V, Q58E, H69K, T74P, V82L/T, N83D or I84V
cDefined by Week 48 response

Analyses of pediatric clinical trial 1182.14 also demonstrated that response to therapy was influenced by the number of baseline protease inhibitor substitutions present.

13 NONCLINICAL TOXICOLOGY

13.1 Carcinogenesis, Mutagenesis, Impairment of Fertility

Long-term carcinogenicity studies in mice and rats have been conducted with tipranavir. Mice were administered 30, 150 or 300 mg/kg/day tipranavir, 150/40 mg/kg/day tipranavir/ritonavir in combination, or 40 mg/kg/day ritonavir. The incidences of benign hepatocellular adenomas and combined adenomas/carcinomas were increased in females of all groups except the low dose of tipranavir. These tumors were also increased in male mice at the high-dose of tipranavir and the tipranavir/ritonavir combination group. Hepatocellular carcinoma incidence was increased in female mice given the high dose of tipranavir and both sexes receiving tipranavir/ritonavir. The combination of tipranavir and ritonavir caused an exposure-related increase in this same tumor type in both sexes. The clinical relevance of the carcinogenic findings in mice is unknown. Systemic exposures in mice (based on AUC or Cmax) at all dose levels tested were below those in humans receiving the recommended dose level. Rats were administered 30, 100 or 300 mg/kg/day tipranavir, 100/26.7 mg/kg/day tipranavir/ritonavir in combination, or 10 mg/kg/day ritonavir. No drug-related findings in male rats were observed. At the highest dose of tipranavir, an increased incidence of benign follicular cell adenomas of the thyroid gland was observed in female rats. Based on AUC measurements, exposure to tipranavir at this dose level in rats is approximately equivalent to exposure in humans at the recommended therapeutic dose. This finding is probably not relevant to humans, because thyroid follicular cell adenomas are considered a rodent-specific effect secondary to enzyme induction.

Tipranavir showed no evidence of mutagenicity or clastogenicity in a battery of five in vitro and in vivo tests including the Ames bacterial reverse mutation assay using S. typhimurium and E. coli, unscheduled DNA synthesis in rat hepatocytes, induction of gene mutation in Chinese hamster ovary cells, a chromosome aberration assay in human peripheral lymphocytes, and a micronucleus assay in mice.

Tipranavir had no effect on fertility or early embryonic development in rats at dose levels up to 1000 mg/kg/day, equivalent to a Cmax of 258 µM in females. Based on Cmax levels in these rats, as well as an exposure (AUC) of 1670 µM∙h in pregnant rats from another study, this exposure was approximately equivalent to the anticipated exposure in humans at the recommended dose level of 500 mg/200 mg APTIVUS/ritonavir BID.

13.2 Animal Toxicology and/or Pharmacology

In preclinical studies in rats, tipranavir treatment induced dose-dependent changes in coagulation parameters (increased prothrombin time, increased activated partial thromboplastin time, and a decrease in some vitamin K dependent factors). In some rats, these changes led to bleeding in multiple organs and death. The co-administration of vitamin E in the form of TPGS (d-alpha-tocopherol polyethylene glycol 1000 succinate) with tipranavir resulted in a significant increase in effects on coagulation parameters, bleeding events, and death.

In preclinical studies of tipranavir in dogs, an effect on coagulation parameters was not seen. Co-administration of tipranavir and vitamin E has not been studied in dogs. Clinical evaluation of coagulation effects on HIV-1-infected subjects demonstrated no tipranavir plus ritonavir effect on coagulation parameters [see Warnings and Precautions (5.5)].

14 CLINICAL STUDIES

14.1 Clinical Trials in Adults

The following clinical data is derived from analyses of 48-week data from studies measuring effects on plasma HIV-1 RNA levels and CD4+ cell counts. At present there are no results from controlled studies evaluating the effect of APTIVUS/ritonavir on clinical progression of HIV-1.

APTIVUS/ritonavir 500 mg/200 mg BID + optimized background regimen (OBR) vs. Comparator Protease Inhibitor/ritonavir BID + OBR

The two clinical trials 1182.12 and 1182.48 (RESIST 1 and RESIST 2) are ongoing, randomized, controlled, open-label, multicenter studies in HIV-1 positive, triple antiretroviral class experienced subjects. All subjects were required to have previously received at least two protease inhibitor-based antiretroviral regimens and were failing a protease inhibitor-based regimen at the time of study entry with baseline HIV-1 RNA at least 1000 copies/mL and any CD4+ cell count. At least one primary protease gene mutation from among 30N, 46I, 46L, 48V, 50V, 82A, 82F, 82L, 82T, 84V or 90M had to be present at baseline, with not more than two mutations at codons 33, 82, 84 or 90.

These studies evaluated treatment response at 48 weeks in a total of 1483 subjects receiving either APTIVUS co-administered with 200 mg of ritonavir plus OBR versus a control group receiving a ritonavir-boosted protease inhibitor (lopinavir, amprenavir, saquinavir or indinavir) plus OBR. Prior to randomization, OBR was individually defined for each subject based on genotypic resistance testing and subject history. The investigator had to declare OBR, comparator protease inhibitor, and use of new enfuvirtide prior to randomization. Randomization was stratified by choice of comparator protease inhibitor and use of new enfuvirtide.

After Week 8, subjects in the control group who met the protocol defined criteria of initial lack of virologic response or confirmed virologic failure had the option of discontinuing treatment and switching to APTIVUS/ritonavir in a separate roll-over study.

Demographics and baseline characteristics were balanced between the APTIVUS/ritonavir arm and control arm. In both studies combined, the 1483 subjects had a median age of 43 years (range 17-80), and were 86.3% male, 75.6% white, 12.9% black, and 0.9% Asian. The median baseline plasma HIV-1 RNA for both treatment groups was 4.8 (range 2.0 to 6.8) log10 copies/mL and median baseline CD4+ cell count was 162 (range 1 to 1894) cells/mm^3. Overall, 38.4% of subjects had a baseline HIV-1 RNA of >100,000 copies/mL, 58.6% had a baseline CD4+ cell count ≤200 cells/mm^3, and 57.8% had experienced an AIDS defining Class C event at baseline.

Subjects had prior exposure to a median of 6 NRTIs, 1 NNRTI, and 4 PIs. A total of 10.1% of subjects had previously used enfuvirtide. In baseline subject samples (n=454), 97% of the HIV-1 isolates were resistant to at least one protease inhibitor, 95% of the isolates were resistant to at least one NRTI, and >75% of the isolates were resistant to at least one NNRTI.

The individually pre-selected protease inhibitor based on genotypic testing and the subject's medical history was lopinavir in 48.7%, amprenavir in 26.4%, saquinavir in 21.8% and indinavir in 3.1% of subjects. A total of 85.1% were possibly resistant or resistant to the pre-selected comparator protease inhibitors. Approximately 21% of subjects used enfuvirtide during the study of which 16.6% in the APTIVUS/ritonavir arm and 13.2% in the comparator/ritonavir arm represented first time use of enfuvirtide (new enfuvirtide).

Treatment response and efficacy outcomes of randomized treatment through Week 48 of studies 1182.12 and 1182.48 are shown in Table 11.

Table 11 Outcomes of Randomized Treatment Through Week 48 (Pooled Studies 1182.12 and 1182.48)
Outcome | APTIVUS/ritonavir (500/200 mg BID) + OBR (N=746) | Comparator Protease Inhibitor*/ritonavir + OBR (N=737)
Virologic Respondersa (confirmed at least 1 log10 HIV-1 RNA below baseline) | 33.8% | 14.9%
Virologic failures | 55.1% | 77.3%
Initial lack of virologic response by Week 8b | 33.0% | 57.9%
Rebound | 18.9% | 16.4%
Never suppressed | 3.2% | 3.0%
Deathc or discontinued due to adverse events | 5.9% | 1.9%
Death | 0.5% | 0.3%
Discontinued due to adverse events | 5.4% | 1.6%
Discontinued due to other reasonsd | 5.2% | 5.8%
*Comparator protease inhibitors were lopinavir, amprenavir, saquinavir or indinavir and 85.1% of subjects were possibly resistant or resistant to the chosen protease inhibitors.
aSubjects achieved and maintained a confirmed ≥1 log10 HIV-1 RNA drop from baseline through Week 48 without prior evidence of treatment failure.
bSubjects did not achieve a 0.5 log10 HIV-1 RNA drop from baseline and did not have viral load <100,000 copies/mL by Week 8.
cDeath only counted if it was the reason for treatment failure.
dIncludes subjects who were lost to-follow-up, withdrawn consent, non-adherent, protocol violations, added/changed background antiretroviral drugs for reasons other than tolerability or toxicity, or discontinued while suppressed.

Through 48 weeks of treatment, the proportion of subjects in the APTIVUS/ritonavir arm compared to the comparator PI/ritonavir arm with HIV-1 RNA <400 copies/mL was 30.3% and 13.6% respectively, and with HIV-1 RNA <50 copies/mL was 22.7% and 10.2% respectively. Among all randomized and treated subjects, the median change from baseline in HIV-1 RNA at the last measurement up to Week 48 was -0.64 log10 copies/mL in subjects receiving APTIVUS/ritonavir versus -0.22 log10 copies/mL in the comparator PI/ritonavir arm.

Among all randomized and treated subjects, the median change from baseline in CD4+ cell count at the last measurement up to Week 48 was +23 cells/mm^3 in subjects receiving APTIVUS/ritonavir (N=740) versus +4 cells/mm^3 in the comparator PI/ritonavir (N=727) arm.

Subjects in the APTIVUS/ritonavir arm achieved a significantly better virologic outcome when APTIVUS/ritonavir was combined with enfuvirtide. Among subjects with new enfuvirtide use, the proportion of subjects in the APTIVUS/ritonavir arm compared to the comparator PI/ritonavir arm with HIV-1 RNA <400 copies/mL was 52.4% and 19.6% respectively, and with HIV-1 RNA <50 copies/mL was 37.3% and 14.4% respectively [see Clinical Pharmacology (12.2) and Microbiology (12.4)]. The median change from baseline in CD4+ cell count at the last measurement up to Week 48 was +89 cells/mm^3 in subjects receiving APTIVUS/ritonavir in combination with newly introduced enfuvirtide (N=124) and +18 cells/mm^3 in the comparator PI/ritonavir (N=96) arm.

14.2 Clinical Trials in Pediatrics

The pharmacokinetic profile, safety and activity of APTIVUS/ritonavir was evaluated in a randomized, open-label, multicenter study. This study enrolled a total of 52 HIV-1 infected, treatment-experienced pediatric subjects 12 to 18 years of age with baseline HIV-1 RNA of at least 1500 copies/mL.

The 52 randomized pediatric subjects had a median age of 15 years (range 12 to 18), and were 53.8% male, 67.3% white, 32.7% black, and 0% Asian. The median baseline plasma HIV-1 RNA was 4.7 (range 2.98 to 6.78) log10 copies/mL and median baseline CD4+ cell count was 318 (range 2 to 650) cells/mm^3. Overall, 63.5% had a baseline CD4+ cell count ≤200 cells/mm^3 and 29.6% had experienced a prior AIDS defining Class C event at baseline. Subjects had prior exposure to a median of 5 NRTIs, 1 NNRTI, and 4 PIs.

At 48 weeks, the overall proportion of subjects 12 to 18 years of age with HIV-1 RNA <400 copies/mL and <50 copies/mL were 33% and 25%, respectively and were similar to adults.

16 HOW SUPPLIED/STORAGE AND HANDLING

APTIVUS capsules 250 mg are pink, oblong soft gelatin capsules imprinted in black with "TPV 250". They are packaged in HDPE unit-of-use bottles with a child resistant closure and 120 capsules. (NDC 0597-0003-02).

Storage

- APTIVUS capsules should be stored in a refrigerator 2°C-8°C (36°F-46°F) prior to opening the bottle. After opening the bottle, the capsules may be stored at 20°C-25°C (68°F-77°F); excursions permitted to 15°C-30°C (59°F-86°F) [see USP Controlled Room Temperature] and must be used within 60 days after first opening of the bottle.

Store in a safe place out of the reach of children.

17 PATIENT COUNSELING INFORMATION

Advise the patient to read the FDA-approved patient labeling (Patient Information).

- Hepatic Impairment and Toxicity

Inform patients that APTIVUS co-administered with 200 mg of ritonavir, has been associated with severe liver disease, including some deaths. Patients with signs or symptoms of clinical hepatitis should discontinue APTIVUS/ritonavir treatment and seek medical evaluation. Symptoms of hepatitis include fatigue, malaise, anorexia, nausea, jaundice, bilirubinuria, acholic stools, liver tenderness or hepatomegaly. Extra vigilance is needed for patients with chronic hepatitis B or C co-infection, as these patients have an increased risk of developing hepatotoxicity.

Liver function tests should be performed prior to initiating therapy with APTIVUS and 200 mg of ritonavir, and frequently throughout the duration of treatment. Patients with chronic hepatitis B or C co-infection or elevations in liver enzymes prior to treatment are at increased risk (approximately 2-fold) for developing further liver enzyme elevations or severe liver disease. Caution should be exercised when administering APTIVUS/ritonavir to patients with liver enzyme abnormalities or history of chronic liver disease. Increased liver function testing is warranted in these patients. APTIVUS should not be given to patients with moderate to severe hepatic impairment.

- Intracranial Hemorrhage

Inform patients that APTIVUS co-administered with 200 mg of ritonavir has been associated with reports of both fatal and non-fatal intracranial hemorrhage. Patients should report any unusual or unexplained bleeding to their physician.

- Drug Interactions

APTIVUS may interact with some drugs; therefore, advise patients to report to their healthcare provider the use of any other prescription or non-prescription medications or herbal products, particularly St. John's wort.

- Rash

Rash, including flat or raised rashes or sensitivity to the sun, have been reported in approximately 10% of subjects receiving APTIVUS. Some patients who developed rash also had one or more of the following symptoms: joint pain or stiffness, throat tightness, generalized itching, muscle aches, fever, redness, blisters, or peeling of the skin. Women taking birth control pills may get a skin rash. Tell patients to discontinue use of APTIVUS and call their physician right away if any of these symptoms develop.

- Sulfa Allergy

Tell patients to report any history of sulfonamide allergy to the physician.

- Contraceptives

Instruct women receiving estrogen-based hormonal contraceptives that additional or alternative contraceptive measures should be used during therapy with APTIVUS. There may be an increased risk of rash when APTIVUS is given with hormonal contraceptives [see Use in Specific Populations (8.3)].

- Fat Redistribution

Inform patients that redistribution or accumulation of body fat may occur in patients receiving antiretroviral therapy and that the cause and long-term health effects of these conditions are not known at this time.

- Administration

Inform patients that APTIVUS must be co-administered with ritonavir to ensure its therapeutic effect. Failure to correctly co-administer APTIVUS with ritonavir will result in reduced plasma levels of tipranavir that may be insufficient to achieve the desired antiviral effect.

- APTIVUS co-administered with ritonavir tablets must only be taken with meals

Instruct patients to swallow APTIVUS capsules whole. They must not be opened or chewed.

Tell patients that sustained decreases in plasma HIV-1 RNA have been associated with a reduced risk of progression to AIDS and death. Patients should remain under the care of a physician while using APTIVUS. Advise patients to take APTIVUS and other concomitant antiretroviral therapy every day as prescribed. APTIVUS, co-administered with ritonavir, must be given in combination with other antiretroviral drugs. Patients should not alter the dose or discontinue therapy without consulting with their healthcare professional. If a dose of APTIVUS is missed, patients should take the dose as soon as possible and then return to their normal schedule. However, if a dose is skipped the patient should not double the next dose.

- Pregnancy Registry

Advise patients that there is a pregnancy exposure registry that monitors pregnancy outcomes in women exposed to APTIVUS during pregnancy [see Use in Specific Populations (8.1)].

- Lactation

Inform individuals with HIV-1 infection that the potential risks of breastfeeding include: (1) HIV 1 transmission (in HIV-1–negative infants), (2) developing viral resistance (in HIV-1–positive infants), and (3) adverse reactions in a breastfed infant similar to those seen in adults [see Use in Specific Populations (8.2)].

Distributed by:
Boehringer Ingelheim Pharmaceuticals, Inc.
Ridgefield, CT 06877 USA

Licensed from:
Boehringer Ingelheim International GmbH

Address medical inquiries to: 1-800-542-6257.

APTIVUS is a registered trademark of and used under license from Boehringer Ingelheim International GmbH.

The other brands listed are trademarks of their respective owners and are not trademarks of Boehringer Ingelheim Pharmaceuticals, Inc.

Copyright © 2024 Boehringer Ingelheim International GmbH

ALL RIGHTS RESERVED

COL9294CD042024
SPL9296E

PATIENT INFORMATION
APTIVUS® (AP-tih-vus)
(tipranavir) capsules

What is the most important information I should know about APTIVUS?
APTIVUS can cause serious side effects, including:

- Liver problems. People who take APTIVUS with ritonavir may develop severe liver disease that can cause death. If you have chronic hepatitis B or C infection, you are at increased risk for liver problems. Your healthcare provider should do blood tests before you start taking APTIVUS with ritonavir and regularly during treatment. If you get any of the following symptoms of liver problems, you should stop taking APTIVUS and ritonavir and tell your healthcare provider right away:

- tiredness
- not feeling well
- loss of appetite
- nausea

- yellowing of your skin or whites of your eyes
- dark (tea-colored) urine
- pale stools (bowel movements)
- pain, ache, or sensitivity on your right side below your ribs

- Bleeding in your brain (intracranial hemorrhage, or ICH). People taking APTIVUS with ritonavir may develop bleeding in the brain that can cause death. Tell your healthcare provider about any unusual or unexplained bleeding during treatment with APTIVUS with ritonavir.

See "What are the possible side effects of APTIVUS?" for more information about side effects.

What is APTIVUS?
APTIVUS is a prescription medicine used with ritonavir and other HIV-1 medicines to treat Human Immunodeficiency Virus-1 (HIV-1) infection in adults and children weighing 79 pounds (36 kg) or higher who:

- have taken HIV-1 medicines in the past, and
- whose healthcare provider determines that they meet certain requirements

HIV-1 is the virus that causes AIDS (Acquired Immune Deficiency Syndrome).

Do not take APTIVUS if you:

- have moderate to severe liver problems
- take any of the following medicines:
  - alfuzosin
  - amiodarone
  - atorvastatin or a product that contains atorvastatin
  - bepridil
  - cisapride
  - ergot-containing medicines:
    - dihydroergotamine
    - ergonovine
    - ergotamine
    - methylergonovine
  - flecainide
  - lovastatin or a product that contains lovastatin
  - lurasidone
  - midazolam, when taken by mouth
  - pimozide
  - propafenone
  - quinidine
  - rifampin
  - sildenafil, when used for the treatment of pulmonary arterial hypertension (PAH)
  - simvastatin or a product that contains simvastatin
  - St. John's wort, or a product that contains St. John's wort
  - triazolam

Serious problems can happen if you take any of these medicines with APTIVUS.

Before taking APTIVUS, tell your healthcare provider about all of your medical conditions, including if you:

- have hemophilia
- have a medical condition that increases your risk of bleeding, including trauma or surgery, or take medicines that increase your risk of bleeding, or take a high dose of vitamin E.
- have liver problems, including hepatitis B or hepatitis C
- have high cholesterol or high triglycerides
- are allergic to sulfa (sulfonamide)
- have diabetes
- are pregnant or plan to become pregnant. It is not known if APTIVUS can harm your unborn baby. Tell your healthcare provider if you become pregnant during treatment with APTIVUS.
  - APTIVUS may reduce how well hormonal birth control (contraceptives) pills work. Women who may become pregnant should use a different form of birth control or an additional barrier method of birth control during treatment with APTIVUS. In addition, there may be an increased risk of rash when APTIVUS is taken with birth control pills.
  Pregnancy Registry: There is a pregnancy registry for women who take APTIVUS during pregnancy. The purpose of this registry is to collect information about the health of you and your baby. Talk to your healthcare provider about how you can take part in this registry.
- are breastfeeding or plan to breastfeed. It is not known if APTIVUS can pass into your breast milk. Talk to your healthcare provider about the following risks of breastfeeding during treatment with APTIVUS:
  - The HIV-1 virus may pass to your baby if your baby does not have the HIV-1 infection
  - The HIV-1 virus may become harder to treat if your baby has HIV-1 infection.
  - Your baby may get side effects from APTIVUS.

Tell your healthcare provider about all the medicines you take including prescription and over-the-counter medicines, vitamins and herbal supplements. Some medicines interact with APTIVUS. Keep a list of your medicines to show your healthcare provider and pharmacist.

- You can ask your healthcare provider or pharmacist for a list of medicines that interact with APTIVUS.
- Do not start taking a new medicine without telling your healthcare provider. Your healthcare provider can tell you if it is safe to take APTIVUS with other medicines.

How should I take APTIVUS?

- Take APTIVUS exactly as your healthcare provider tells you.
- You must take APTIVUS at the same time you take ritonavir.
- APTIVUS taken with ritonavir tablets must only be taken with meals.
- Take 2 APTIVUS capsules with your prescribed dose of ritonavir twice a day.
- Swallow APTIVUS capsules whole. Do not open or chew the capsules.
- APTIVUS taken with ritonavir must be used together with other HIV-1 medicines.
- Do not change your dose or stop taking APTIVUS without talking to your healthcare provider.
- Stay under the care of your healthcare provider during treatment with APTIVUS.
- If you forget to take APTIVUS, take the next dose of APTIVUS together with ritonavir as soon as you remember. Take your next dose of APTIVUS at your normal time. Do not take a double dose to make up for a missed dose.
- When your APTIVUS supply starts to run low, get more from your healthcare provider or pharmacy. This is very important because the amount of virus in your blood may increase if the medicine is stopped for even a short time. The virus may develop resistance to APTIVUS and become harder to treat.
- If you take too much APTIVUS, call your healthcare provider or go to the nearest hospital emergency room right away.

What are the possible side effects of APTIVUS?

APTIVUS may cause serious side effects, including:

- See "What is the most important information I should know about APTIVUS?"
- Rash. Some people who take APTIVUS can get a rash including flat or raised rashes or sensitivity to the sun. Women taking hormonal therapy (birth control pills or hormonal replacement therapy) may be at an increased risk of getting a skin rash. If you get any of the following symptoms, stop taking APTIVUS and call your healthcare provider right away:

- joint pain or stiffness
- throat tightness
- itching
- muscle aches

- fever
- redness
- blisters
- peeling of the skin

- Diabetes and high blood sugar (hyperglycemia). Some people who take protease inhibitors including APTIVUS can get high blood sugar, develop diabetes, or your diabetes can get worse. Tell your healthcare provider if you notice an increase in thirst or if you start urinating more often during treatment with APTIVUS.
- Changes in your immune system (Immune Reconstitution Syndrome) can happen when you start taking HIV-1 medicines. Your immune system may get stronger and begin to fight infections that have been hidden in your body for a long time. Tell your healthcare provider right away if you start having new symptoms after starting your HIV-1 medicine.
- Changes in body fat can happen in people who take HIV-1 medicines. The changes may include an increased amount of fat in the upper back and neck ("buffalo hump"), breast, and around the middle of your body (trunk). Loss of fat from the legs, arms, and face may also happen. The exact cause and long-term health effects of these conditions are not known.
- Increased blood fat (lipid) levels. Some people who take APTIVUS with ritonavir have increases in blood fat levels (cholesterol and triglycerides). Your healthcare provider will do blood tests to monitor your blood fat levels before you start taking and during treatment of APTIVUS with ritonavir.
- Increased bleeding in people with hemophilia. Some people with hemophilia have increased bleeding with protease inhibitors including APTIVUS.

The most common side effects of APTIVUS in adults include:

- diarrhea
- nausea
- fever
- vomiting

- tiredness
- headache
- stomach pain

The most common side effects of APTIVUS in children were the same as those seen in adults. Rash was seen more frequently in children than in adults.
These are not all of the possible side effects of APTIVUS.
Call your doctor for medical advice about side effects. You may report side effects to FDA at 1-800-FDA-1088.

How should I store APTIVUS?

- Store unopened bottles of APTIVUS capsules in a refrigerator at 36°F to 46°F (2°C to 8°C).
- After opening the bottle of APTIVUS, the capsules may be stored at room temperature between 68°F to 77°F (20°C to 25°C) and must be used within 60 days after first opening of the bottle.
- APTIVUS capsules come in a bottle with a child resistant closure.

Keep APTIVUS and all medicines out of the reach of children.

General information about the safe and effective use of APTIVUS.
Medicines are sometimes prescribed for purposes other than those listed in a Patient Information leaflet. Do not use APTIVUS for a condition for which it was not prescribed. Do not give APTIVUS to other people, even if they have the same condition you have. It may harm them. You can ask your pharmacist or healthcare professional for information about APTIVUS that is written for health professionals.

What are the ingredients in APTIVUS?
Active Ingredient: tipranavir
Major Inactive Ingredients: dehydrated alcohol, polyoxyl 35 castor oil, propylene glycol, mono/diglycerides of caprylic/capric acid, and gelatin.
Distributed by: Boehringer Ingelheim Pharmaceuticals, Inc. Ridgefield, CT 06877 USA
Licensed from: Boehringer Ingelheim International GmbH
APTIVUS is a registered trademark of and used under license from Boehringer Ingelheim International GmbH.
The other brands listed are trademarks of their respective owners and are not trademarks of Boehringer Ingelheim Pharmaceuticals, Inc.
Copyright © 2024 Boehringer Ingelheim International GmbH
ALL RIGHTS RESERVED
COL9294CD042024
For current prescribing information, scan the code or for additional information, you may also call Boehringer Ingelheim Pharmaceuticals, Inc. at 1-800-542-6257.

This Patient Information has been approved by the U.S. Food and Drug Administration.

Revised: 04/2024

PRINCIPAL DISPLAY PANEL - 250 mg Capsule Bottle Label

NDC 0597-0003-02

Aptivus®
(tipranavir)
Capsules 250 mg

120 capsules
Unit of Use Container

Each capsule contains 250 mg tipranavir and
7% w/w dehydrated alcohol (0.1 g per capsule).

ALERT
Find out about medicines that should
not be taken with Aptivus

Note to Pharmacist: Do not cover
ALERT box with Pharmacy label

Boehringer
Ingelheim

Rx only